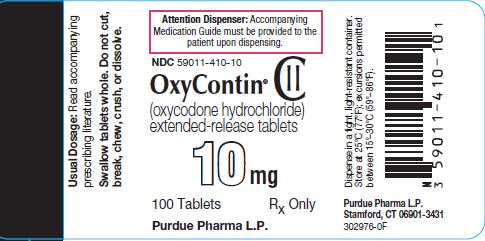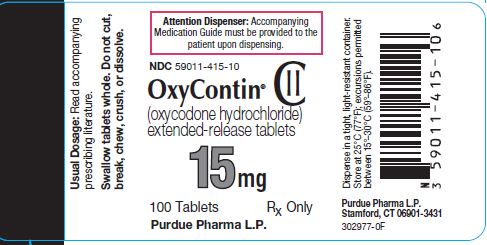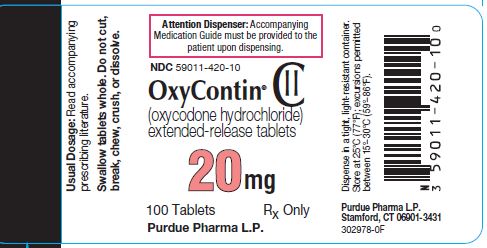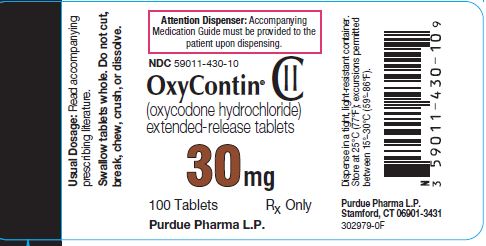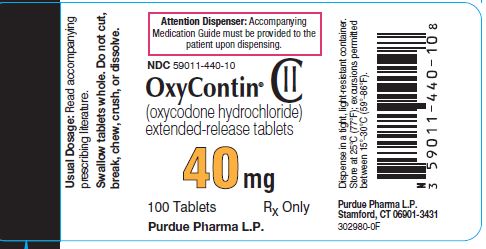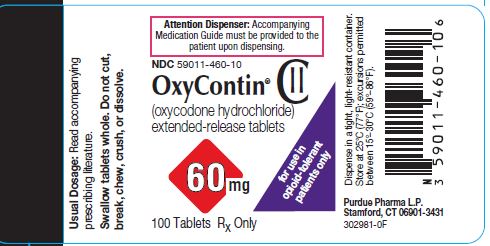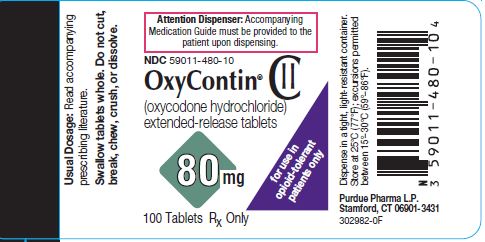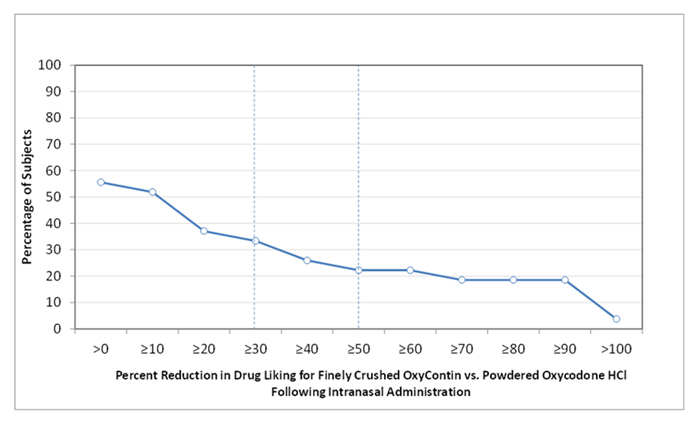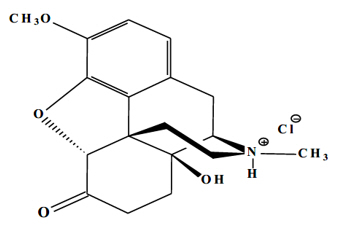 DRUG LABEL: OxyContin
NDC: 59011-480 | Form: TABLET, FILM COATED, EXTENDED RELEASE
Manufacturer: Purdue Pharma LP
Category: prescription | Type: HUMAN PRESCRIPTION DRUG LABEL
Date: 20260130
DEA Schedule: CII

ACTIVE INGREDIENTS: OXYCODONE HYDROCHLORIDE 80 mg/1 1
INACTIVE INGREDIENTS: BUTYLATED HYDROXYTOLUENE; HYPROMELLOSE, UNSPECIFIED; POLYETHYLENE GLYCOL 400; MAGNESIUM STEARATE; TITANIUM DIOXIDE; FERRIC OXIDE YELLOW; FD&C BLUE NO. 2; ALUMINUM OXIDE; HYDROXYPROPYL CELLULOSE, UNSPECIFIED

HIGHLIGHTS OF PRESCRIBING INFORMATION

These highlights do not include all the information needed to use OXYCONTIN® safely and effectively. See full prescribing information for OXYCONTIN.
OXYCONTIN® (oxycodone hydrochloride) extended-release tablets, for oral use, CII
Initial U.S. Approval: 1950

WARNING: SERIOUS AND LIFE-THREATENING RISKS FROM USE OF OXYCONTIN

See full prescribing information for complete boxed warning.

- OXYCONTIN exposes users to risks of addiction, abuse, and misuse, which can lead to overdose and death. Assess patient's risk before prescribing and reassess regularly for these behaviors and conditions. (5.1)
- Serious, life-threatening, or fatal respiratory depression may occur. Monitor closely, especially upon initiation or following a dosage increase. To reduce the risk of respiratory depression, proper dosing and titration of OXYCONTIN are essential. Instruct patients to swallow OXYCONTIN tablets whole to avoid exposure to a potentially fatal dose of oxycodone. (5.2)
- Accidental ingestion of OXYCONTIN, especially by children, can result in a fatal overdose of oxycodone. (5.2)
- Concomitant use of opioids with benzodiazepines or other central nervous system (CNS) depressants, including alcohol, may result in profound sedation, respiratory depression, coma, and death. Reserve concomitant prescribing for use in patients for whom alternative treatment options are inadequate. (5.3, 7)
- Advise pregnant women using opioids for an extended period of time of the risk of Neonatal Opioid Withdrawal Syndrome, which may be life-threatening if not recognized and treated. Ensure that appropriate management by neonatology experts will be available at delivery. (5.4)
- Healthcare providers are strongly encouraged to complete a REMS-compliant education program and to counsel patients and caregivers on serious risks, safe use, and the importance of reading the Medication Guide with each prescription. (5.5)
- Concomitant use with CYP3A4 inhibitors (or discontinuation of CYP3A4 inducers) can result in a fatal overdose of oxycodone. (5.6, 7, 12.3)

RECENT MAJOR CHANGES

Boxed Warning | 12/2025
Indications and Usage (1) | 12/2025
Dosage and Administration (2.2, 2.3) | 12/2025
Warnings and Precautions (5.1, 5.2, 5.3, 5.13, 5.15) | 12/2025

1 INDICATIONS AND USAGE

- OXYCONTIN is an opioid agonist indicated for the management of severe and persistent pain that requires an opioid analgesic that cannot be adequately treated with alternative options, including immediate-release opioids in:
- Adults (1); and
- Opioid-tolerant pediatric patients 11 years of age and older who are already receiving and tolerate a minimum daily opioid dose of at least 20 mg oxycodone orally or its equivalent. (1)

Limitations of Use

- Because of the risks of addiction, abuse, misuse, overdose, and death, which can occur at any dosage or duration and persist over the course of therapy, reserve opioid analgesics, including OXYCONTIN, for use in patients for whom alternative treatment options are ineffective, not tolerated, or would be otherwise inadequate to provide sufficient management of pain. (1, 5.1)
- OXYCONTIN is not indicated as an as-needed (prn) analgesic. (1)

2 DOSAGE AND ADMINISTRATION

- OXYCONTIN should be prescribed only by healthcare professionals who are knowledgeable about the use of extended-release/long-acting opioids and how to mitigate the associated risks. (2.1)
- OXYCONTIN 60 mg and 80 mg tablets, a single dose greater than 40 mg, or a total daily dose greater than 80 mg are only for use in patients in whom tolerance to an opioid of comparable potency has been established. (2.1)
- Patients considered opioid-tolerant are those taking, for one week or longer, at least 60 mg oral morphine per day, 25 mcg transdermal fentanyl per hour, 30 mg oral oxycodone per day, 8 mg oral hydromorphone per day, 25 mg oral oxymorphone per day, 60 mg oral hydrocodone per day, or an equianalgesic dose of another opioid. (2.1)
- Use the lowest effective dosage for the shortest duration of time consistent with individual patient treatment goals. Reserve titration to higher doses of OXYCONTIN for patients in whom lower doses are insufficiently effective and in whom the expected benefits of using a higher dose opioid clearly outweigh the substantial risks. (2.1, 5)
- Initiate the dosing regimen for each patient individually, taking into account the patient's underlying cause and severity of pain, prior analgesic treatment and response, and risk factors for addiction, abuse, and misuse. (2.1, 5.1)
- Respiratory depression can occur at any time during opioid therapy, especially when initiating and following dosage increases with OXYCONTIN. Consider this risk when selecting an initial dose and when making dose adjustments. (2.1, 5.2)
- OXYCONTIN is administered orally every 12 hours. (2.1)
- Instruct patients to swallow tablets intact and not to cut, break, chew, crush, or dissolve tablets (risk of potentially fatal dose). (2.1, 5.1)
- Instruct patients to take tablets one at a time, with enough water to ensure complete swallowing immediately after placing in mouth. (2.1, 5.12)
- Discuss opioid overdose reversal agents and options for acquiring them with the patient and/or caregiver, both when initiating and renewing treatment with OXYCONTIN, especially if the patient has additional risk factors for overdose, or close contacts at risk for exposure and overdose. (2.2, 5.1, 5.2, 5.3)
- Periodically reassess patients receiving OXYCONTIN to evaluate the continued need for opioid analgesics to maintain pain control, for the signs or symptoms of adverse reactions, and for the development of addiction, abuse, or misuse. (2.4)
- Do not rapidly reduce or abruptly discontinue OXYCONTIN in a physically-dependent patient because rapid reduction or abrupt discontinuation of opioid analgesics has resulted in serious withdrawal symptoms, uncontrolled pain, and suicide. (2.9, 5.15)

Adults: For patients who are not opioid tolerant, initiate with 10 mg tablets orally every 12 hours. See full prescribing information for instructions on conversion from other opioids to OXYCONTIN, titration and maintenance of therapy. (2.3, 2.5)

Pediatric Patients 11 Years of Age and Older:

- For use only in pediatric patients 11 years and older already receiving and tolerating opioids for at least 5 consecutive days with a minimum of 20 mg per day of oxycodone or its equivalent for at least two days immediately preceding dosing with OXYCONTIN. (2.4)
- See full prescribing information for instructions on conversion from other opioids to OXYCONTIN, titration and maintenance of therapy. (2.4, 2.5)

Geriatric Patients: In debilitated, opioid non-tolerant geriatric patients, initiate dosing at one third to one half the recommended starting dosage and titrate carefully. (2.7, 8.5)

Patients with Hepatic Impairment: Initiate dosing at one third to one half the recommended starting dosage and titrate carefully. (2.8, 8.6)

3 DOSAGE FORMS AND STRENGTHS

Extended-release tablets: 10 mg, 15 mg, 20 mg, 30 mg, 40 mg, 60 mg, and 80 mg. (3)

4 CONTRAINDICATIONS

- Significant respiratory depression (4)
- Acute or severe bronchial asthma in an unmonitored setting or in absence of resuscitative equipment (4)
- Known or suspected gastrointestinal obstruction, including paralytic ileus (4)
- Hypersensitivity to oxycodone (4)

5 WARNINGS AND PRECAUTIONS

- Opioid-Induced Hyperalgesia and Allodynia: Opioid-Induced Hyperalgesia (OIH) occurs when an opioid analgesic paradoxically causes an increase in pain, or an increase in sensitivity to pain. If OIH is suspected, carefully consider appropriately decreasing the dose of the current opioid analgesic, or opioid rotation. (5.7)
- Life-Threatening Respiratory Depression in Patients with Chronic Pulmonary Disease or in Elderly, Cachectic, or Debilitated Patients: Regularly evaluate, particularly during initiation and titration. (5.8)
- Adrenal Insufficiency: If diagnosed, treat with physiologic replacement of corticosteroids, and wean patient off of the opioid. (5.9)
- Severe Hypotension: Regularly evaluate during dosage initiation and titration. Avoid use of OXYCONTIN in patients with circulatory shock. (5.10)
- Risks of Use in Patients with Increased Intracranial Pressure, Brain Tumors, Head Injury, or Impaired Consciousness: Monitor for sedation and respiratory depression. Avoid use of OXYCONTIN in patients with impaired consciousness or coma. (5.11)
- Risk of Obstruction in Patients who have Difficulty Swallowing or have Underlying GI Disorders that may Predispose them to Obstruction: Consider use of an alternative analgesic. (5.12)

6 ADVERSE REACTIONS

Most common adverse reactions (incidence >5%) were constipation, nausea, somnolence, dizziness, vomiting, pruritus, headache, dry mouth, asthenia, and sweating. (6.1)

To report SUSPECTED ADVERSE REACTIONS, contact Purdue Pharma L.P. at 1-888-726-7535 or FDA at 1-800-FDA-1088 or www.fda.gov/medwatch.

7 DRUG INTERACTIONS

- CNS Depressants: Concomitant use may cause hypotension, profound sedation, respiratory depression, coma, and death. If coadministration is required and the decision to begin OXYCONTIN is made, start with 1/3 to 1/2 the recommended starting dosage, consider using a lower dosage of the concomitant CNS depressant, and frequently evaluate. (2.6, 5.3, 7)
- Serotonergic Drugs: Concomitant use may result in serotonin syndrome. Discontinue OXYCONTIN if serotonin syndrome is suspected. (7)
- Mixed Agonist/Antagonist and Partial Agonist Opioid Analgesics: Avoid use with OXYCONTIN because they may reduce analgesic effect of OXYCONTIN or precipitate withdrawal symptoms. (5.15, 7)
- Monoamine Oxidase Inhibitors (MAOIs): Can potentiate the effects of morphine. Avoid concomitant use in patients receiving MAOIs or within 14 days of stopping treatment with an MAOI. (7)

8 USE IN SPECIFIC POPULATIONS

Pregnancy: May cause fetal harm. (8.1)

Lactation: Not recommended. (8.2)

FULL PRESCRIBING INFORMATION

WARNING: SERIOUS AND LIFE-THREATENING RISKS FROM USE OF OXYCONTIN

Addiction, Abuse, and Misuse

Because the use of OXYCONTIN exposes patients and other users to the risks of opioid addiction, abuse, and misuse, which can lead to overdose and death, assess each patient's risk prior to prescribing and reassess all patients regularly for the development of these behaviors and conditions [see Warnings and Precautions (5.1)].

Life-Threatening Respiratory Depression

Serious, life-threatening, or fatal respiratory depression may occur with use of OXYCONTIN, especially during initiation or following a dosage increase. To reduce the risk of respiratory depression, proper dosing and titration of OXYCONTIN are essential. Instruct patients to swallow OXYCONTIN tablets whole; crushing, chewing, or dissolving OXYCONTIN tablets can cause rapid release and absorption of a potentially fatal dose of oxycodone [see Warnings and Precautions (5.2)].

Accidental Ingestion

Accidental ingestion of even one dose of OXYCONTIN, especially by children, can result in a fatal overdose of oxycodone [see Warnings and Precautions (5.2)].

Risks From Concomitant Use With Benzodiazepines Or Other CNS Depressants

Concomitant use of opioids with benzodiazepines or other central nervous system (CNS) depressants, including alcohol, may result in profound sedation, respiratory depression, coma, and death. Reserve concomitant prescribing of OXYCONTIN and benzodiazepines or other CNS depressants for use in patients for whom alternative treatment options are inadequate [see Warnings and Precautions (5.3), Drug Interactions (7)].

Neonatal Opioid Withdrawal Syndrome (NOWS)

Advise pregnant women using opioids for an extended period of time of the risk of Neonatal Opioid Withdrawal Syndrome, which may be life-threatening if not recognized and treated. Ensure that management by neonatology experts will be available at delivery [see Warnings and Precautions (5.4)].

Opioid Analgesic Risk Evaluation and Mitigation Strategy (REMS)

Healthcare providers are strongly encouraged to complete a REMS-compliant education program and to counsel patients and caregivers on serious risks, safe use, and the importance of reading the Medication Guide with each prescription [see Warnings and Precautions (5.5)].

Cytochrome P450 3A4 Interaction

The concomitant use of OXYCONTIN with all cytochrome P450 3A4 inhibitors may result in an increase in oxycodone plasma concentrations, which could increase or prolong adverse drug effects and may cause potentially fatal respiratory depression. In addition, discontinuation of a concomitantly used cytochrome P450 3A4 inducer may result in an increase in oxycodone plasma concentration. Regularly evaluate patients receiving OXYCONTIN and any CYP3A4 inhibitor or inducer [see Warnings and Precautions (5.6), Drug Interactions (7), Clinical Pharmacology (12.3)].

1 INDICATIONS AND USAGE

OXYCONTIN is indicated for the management of severe and persistent pain that requires an opioid analgesic and that cannot be adequately treated with alternative options, including immediate-release opioids, in:

- Adults; and
- Opioid-tolerant pediatric patients 11 years of age and older who are already receiving and tolerate a minimum daily opioid dose of at least 20 mg oxycodone orally or its equivalent.

Limitations of Use

- Because of the risks of addiction, abuse, misuse, overdose, and death, which can occur at any dosage or duration and persist over the course of therapy [see Warnings and Precautions (5.1)], reserve opioid analgesics, including OXYCONTIN, for use in patients for whom alternative treatment options are ineffective, not tolerated, or would be otherwise inadequate to provide sufficient management of pain.
- OXYCONTIN is not indicated as an as-needed (prn) analgesic.

2 DOSAGE AND ADMINISTRATION

2.1 Important Dosage and Administration Instructions

- OXYCONTIN should be prescribed only by healthcare professionals who are knowledgeable about the use of extended-release/long-acting opioids and how to mitigate the associated risks.
- OXYCONTIN 60 mg and 80 mg tablets, a single dose greater than 40 mg, or a total daily dose greater than 80 mg are only for use in patients in whom tolerance to an opioid of comparable potency has been established. Adult patients who are opioid- tolerant are those receiving, for one week or longer, at least 60 mg oral morphine per day, 25 mcg transdermal fentanyl per hour, 30 mg oral oxycodone per day, 8 mg oral hydromorphone per day, 25 mg oral oxymorphone per day, 60 mg oral hydrocodone per day, or an equianalgesic dose of another opioid.
- Use the lowest effective dosage for the shortest duration of time consistent with individual patient treatment goals [see Warnings and Precautions (5)]. Because the risk of overdose increases as opioid doses increase, reserve titration to higher doses of OXYCONTIN for patients in whom lower doses are insufficiently effective and in whom the expected benefits of using a higher dose opioid clearly outweigh the substantial risks.
- Initiate the dosing regimen for each patient individually, taking into account the patient's underlying cause and severity of pain, prior analgesic treatment and response, and risk factors for addiction, abuse, and misuse [see Warnings and Precautions (5.1)].
- Respiratory depression can occur at any time during opioid therapy, especially when initiating and following dosage increases with OXYCONTIN. Consider this risk when selecting an initial dose and when making dose adjustments [see Warnings and Precautions (5.2)].
- OXYCONTIN is administered orally every 12 hours.
- Instruct patients to swallow OXYCONTIN tablets whole, one tablet at a time, with enough water to ensure complete swallowing immediately after placing in the mouth. Instruct patients not to pre-soak, lick, or otherwise wet the tablet prior to placing in the mouth [see Warnings and Precautions (5.12)]. Cutting, breaking, crushing, chewing, or dissolving OXYCONTIN tablets will result in uncontrolled delivery of oxycodone and can lead to overdose or death [see Warnings and Precautions (5.1)].

2.2 Patient Access to an Opioid Overdose Reversal Agent for the Emergency Treatment of Opioid Overdose

Inform patients and caregivers about opioid overdose reversal agents (e.g., naloxone, nalmefene). Discuss the importance of having access to an opioid overdose reversal agent, especially if the patient has risk factors for overdose (e.g., concomitant use of CNS depressants, a history of opioid use disorder, or prior opioid overdose) or if there are household members (including children) or other close contacts at risk for accidental ingestion or opioid overdose. The presence of risk factors for overdose should not prevent the management of pain in any patient [see Warnings and Precautions (5.1, 5.2, 5.3)].

Discuss the options for obtaining an opioid overdose reversal agent (e.g., prescription, over-the-counter, or as part of a community-based program) [see Warnings and Precautions (5.2)].

There are important differences among the opioid overdose reversal agents, such as route of administration, product strength, approved patient age range, and pharmacokinetics. Be familiar with these differences, as outlined in the approved labeling for those products, prior to recommending or prescribing such an agent.

2.3 Initial Dosage in Adults

It is safer to underestimate a patient's 24-hour oral oxycodone requirements and provide rescue medication (e.g., immediate-release opioid) than to overestimate the 24-hour oral oxycodone dosage and manage an adverse reaction due to an overdose. While useful tables of opioid equivalents are readily available, there is substantial inter-patient variability in the relative potency of different opioids. Frequently reevaluate patients for signs and symptoms of opioid withdrawal and for signs of oversedation/toxicity after converting patients to OXYCONTIN.

Use of OXYCONTIN in Adults who are not Opioid Tolerant

The starting dosage for adults who are not opioid tolerant is OXYCONTIN 10 mg orally every 12 hours. Use of higher starting doses in patients who are not opioid tolerant may cause fatal respiratory depression [see Warnings and Precautions (5.2)].

Conversion from Other Oral Oxycodone Formulations to OXYCONTIN

If switching from other oral oxycodone formulations to OXYCONTIN, administer one half of the patient's total daily oral oxycodone dose as OXYCONTIN every 12 hours.

Conversion from Methadone to OXYCONTIN

Regular evaluation is of particular importance when converting from methadone to other opioid agonists. The ratio between methadone and other opioid agonists may vary widely as a function of previous dose exposure. Methadone has a long half-life and can accumulate in the plasma.

Conversion from Fentanyl Transdermal System to OXYCONTIN

Treatment with OXYCONTIN can be initiated after the fentanyl transdermal system has been removed for at least 18 hours. Although there has been no systematic assessment of such conversion, start with a conservative conversion: substitute 10 mg of OXYCONTIN every 12 hours for each 25 mcg per hour fentanyl transdermal system. Follow the patient closely during conversion from fentanyl transdermal system to OXYCONTIN, as there is limited documented experience with this conversion.

Conversion from Other Opioid Analgesics to OXYCONTIN

When OXYCONTIN therapy is initiated, discontinue all other opioid analgesics other than those used on an as needed basis for breakthrough pain when appropriate.

There are no established conversion ratios for conversion from other opioids to OXYCONTIN defined by clinical trials. Initiate dosing using OXYCONTIN 10 mg orally every 12 hours.

2.4 Initial Dosage in Pediatric Patients 11 Years and Older

The following dosing information is for use only in pediatric patients 11 years and older already receiving and tolerating opioids for at least five consecutive days. For the two days immediately preceding dosing with OXYCONTIN, patients must be taking a minimum of 20 mg per day of oxycodone or its equivalent. OXYCONTIN is not appropriate for use in pediatric patients requiring less than a 20 mg total daily dose. Table 1, based on clinical trial experience, displays the conversion factor when switching pediatric patients 11 years and older (under the conditions described above) from opioids to OXYCONTIN.

When OXYCONTIN therapy is initiated, discontinue all opioid analgesics other than those used on an as needed basis for breakthrough pain when appropriate.

There is substantial inter-patient variability in the relative potency of different opioid drugs and formulations. Therefore, a conservative approach is advised when determining the total daily dosage of OXYCONTIN. It is safer to underestimate a patient's 24-hour oral oxycodone requirements and provide rescue medication (e.g., immediate-release opioid) than to overestimate the 24-hour oral oxycodone requirements and manage an adverse reaction due to an overdose.

Consider the following when using the information in Table 1.

- This is not a table of equianalgesic doses.
- The conversion factors in this table are only for the conversion from one of the listed oral opioid analgesics to OXYCONTIN.
- The table cannot be used to convert from OXYCONTIN to another opioid. Doing so will result in an over-estimation of the dose of the new opioid and may result in a fatal overdose.
- The formula for conversion from prior opioids, including oral oxycodone, to the daily dose of OXYCONTIN is mg per day of prior opioid x factor = mg per day of OXYCONTIN. Divide the calculated total daily dose by 2 to get the every-12-hour OXYCONTIN dose. If rounding is necessary, always round the dose down to the nearest OXYCONTIN tablet strength available.

Table 1: Conversion Factors When Switching Pediatric Patients 11 Years and Older to OXYCONTIN
Prior Opioid | Conversion Factor
 | Oral | Parenteral [For patients receiving high-dose parenteral opioids, a more conservative conversion is warranted. For example, for high-dose parenteral morphine, use 1.5 instead of 3 as a multiplication factor.]
Oxycodone | 1 | --
Hydrocodone | 0.9 | --
Hydromorphone | 4 | 20
Morphine | 0.5 | 3
Tramadol | 0.17 | 0.2

Step #1: To calculate the estimated total OXYCONTIN daily dosage using Table 1:

- For pediatric patients taking a single opioid, sum the current total daily dosage of the opioid and then multiply the total daily dosage by the approximate conversion factor to calculate the approximate OXYCONTIN daily dosage.
- For pediatric patients on a regimen of more than one opioid, calculate the approximate oxycodone dose for each opioid and sum the totals to obtain the approximate OXYCONTIN daily dosage.
- For pediatric patients on a regimen of fixed-ratio opioid/non-opioid analgesic products, use only the opioid component of these products in the conversion.

Step #2: If rounding is necessary, always round the dosage down to the nearest OXYCONTIN tablet strength available and initiate OXYCONTIN therapy with that dose. If the calculated OXYCONTIN total daily dosage is less than 20 mg, there is no safe strength for conversion and do not initiate OXYCONTIN.

Example conversion from a single opioid (e.g., hydrocodone) to OXYCONTIN: Using the conversion factor of 0.9 for oral hydrocodone in Table 1, a total daily hydrocodone dosage of 50 mg is converted to 45 mg of oxycodone per day or 22.5 mg of OXYCONTIN every 12 hours. After rounding down to the nearest strength available, the recommended OXYCONTIN starting dosage is 20 mg every 12 hours.

Step #3: Close observation and titration are warranted until pain management is stable on the new opioid. Monitor patients for signs and symptoms of opioid withdrawal or for signs of over-sedation/toxicity after converting patients to OXYCONTIN [see Dosage and Administration (2.5)] for important instructions on titration and maintenance of therapy.

There is limited experience with conversion from transdermal fentanyl to OXYCONTIN in pediatric patients 11 years and older. If switching from transdermal fentanyl patch to OXYCONTIN, ensure that the patch has been removed for at least 18 hours prior to starting OXYCONTIN. Although there has been no systematic assessment of such conversion, start with a conservative conversion: substitute 10 mg of OXYCONTIN every 12 hours for each 25 mcg per hour fentanyl transdermal patch. Follow the patient closely during conversion from transdermal fentanyl to OXYCONTIN.

If using asymmetric dosing, instruct patients to take the higher dose in the morning and the lower dose in the evening.

2.5 Titration and Maintenance of Therapy in Adults and Pediatric Patients 11 Years and Older

Individually titrate OXYCONTIN to a dosage that provides adequate analgesia and minimizes adverse reactions. Continually reevaluate patients receiving OXYCONTIN to assess the maintenance of pain control, signs and symptoms of opioid withdrawal, and other adverse reactions, as well as to reassess for the development of addiction, abuse and misuse [see Warnings and Precautions (5.1, 5.15)]. Frequent communication is important among the prescriber, other members of the healthcare team, the patient, and the caregiver/family during periods of changing analgesic requirements, including initial titration. During use of opioid therapy for an extended period of time, periodically reassess the continued need for the use of opioid analgesics.

Patients who experience breakthrough pain may require a dosage adjustment of OXYCONTIN or may need rescue medication with an appropriate dose of an immediate-release analgesic. If the level of pain increases after dose stabilization, attempt to identify the source of increased pain before increasing the OXYCONTIN dosage. Because steady-state plasma concentrations are approximated in 1 day, OXYCONTIN dosage may be adjusted every 1 to 2 days.

If after increasing the dosage, unacceptable opioid-related adverse reactions are observed (including an increase in pain after a dosage increase), consider reducing the dosage [see Warnings and Precautions (5)]. Adjust the dosage to obtain an appropriate balance between management of pain and opioid-related adverse reactions.

There are no well-controlled clinical studies evaluating the safety and efficacy with dosing more frequently than every 12 hours. As a guideline for pediatric patients 11 years and older, the total daily oxycodone dosage usually can be increased by 25% of the current total daily dosage. As a guideline for adults, the total daily oxycodone dosage usually can be increased by 25% to 50% of the current total daily dosage, each time an increase is clinically indicated.

2.6 Dosage Modifications with Concomitant Use of Central Nervous System Depressants

If the patient is currently taking a central nervous system (CNS) depressant and the decision is made to begin OXYCONTIN, start with one-third to one-half the recommended starting dosage of OXYCONTIN, consider using a lower dosage of the concomitant CNS depressant, and regularly evaluate patients for signs of respiratory depression, sedation, and hypotension [see Warnings and Precautions (5.3), Drug Interactions (7)].

2.7 Dosage Modifications in Geriatric Patients who are Debilitated and not Opioid-Tolerant

For geriatric patients who are debilitated and not opioid-tolerant, start dosing patients at one-third to one-half the recommended starting dosage and titrate the dosage cautiously. Regularly evaluate for signs of respiratory depression, sedation, and hypotension [see Use in Specific Populations (8.5)].

2.8 Dosage Modifications in Patients with Hepatic Impairment

For patients with hepatic impairment, start dosing patients at one-third to one-half the recommended starting dosage and titrate the dosage carefully. Regularly evaluate for signs of respiratory depression, sedation, and hypotension [see Use in Specific Populations (8.6), Clinical Pharmacology (12.3)].

2.9 Safe Reduction or Discontinuation of OXYCONTIN

Do not rapidly reduce or abruptly discontinue OXYCONTIN in patients who may be physically dependent on opioids. Rapid reduction or abrupt discontinuation of opioid analgesics in patients who are physically dependent on opioids has resulted in serious withdrawal symptoms, uncontrolled pain, and suicide. Rapid reduction or abrupt discontinuation has also been associated with attempts to find other sources of opioid analgesics, which may be confused with drug-seeking for abuse. Patients may also attempt to treat their pain or withdrawal symptoms with illicit opioids, such as heroin, and other substances.

When a decision has been made to decrease the dose or discontinue therapy in an opioid-dependent patient taking OXYCONTIN, there are a variety of factors that should be considered, including the total daily dose of opioid (including OXYCONTIN) the patient has been taking, the duration of treatment, the type of pain being treated, and the physical and psychological attributes of the patient. It is important to ensure ongoing care of the patient and to agree on an appropriate tapering schedule and follow-up plan so that patient and provider goals and expectations are clear and realistic. When opioid analgesics are being discontinued due to a suspected substance use disorder, evaluate and treat the patient, or refer for evaluation and treatment of the substance use disorder. Treatment should include evidence-based approaches, such as medication assisted treatment of opioid use disorder. Complex patients with comorbid pain and substance use disorders may benefit from referral to a specialist.

There are no standard opioid tapering schedules that are suitable for all patients. Good clinical practice dictates a patient-specific plan to taper the dose of the opioid gradually. For patients on OXYCONTIN who are physically opioid-dependent, initiate the taper by a small enough increment (e.g., no greater than 10% to 25% of the total daily dose) to avoid withdrawal symptoms, and proceed with dose-lowering at an interval of every 2 to 4 weeks. Patients who have been taking opioids for briefer periods of time may tolerate a more rapid taper.

It may be necessary to provide the patient with lower dosage strengths to accomplish a successful taper. Reassess the patient frequently to manage pain and withdrawal symptoms, should they emerge. Common withdrawal symptoms include restlessness, lacrimation, rhinorrhea, yawning, perspiration, chills, myalgia, and mydriasis. Other signs and symptoms also may develop, including irritability, anxiety, backache, joint pain, weakness, abdominal cramps, insomnia, nausea, anorexia, vomiting, diarrhea, or increased blood pressure, respiratory rate, or heart rate. If withdrawal symptoms arise, it may be necessary to pause the taper for a period of time or raise the dose of the opioid analgesic to the previous dose, and then proceed with a slower taper. In addition, evaluate patients for any changes in mood, emergence of suicidal thoughts, or use of other substances.

When managing patients taking opioid analgesics, particularly those who have been treated for an extended period of time and/or with high doses for chronic pain, ensure that a multimodal approach to pain management, including mental health support (if needed), is in place prior to initiating an opioid analgesic taper. A multimodal approach to pain management may optimize the treatment of chronic pain, as well as assist with the successful tapering of the opioid analgesic [see Warnings and Precautions (5.15), Drug Abuse and Dependence (9.3)].

3 DOSAGE FORMS AND STRENGTHS

Extended-release tablets: 10 mg, 15 mg, 20 mg, 30 mg, 40 mg, 60 mg, and 80 mg.

- 10 mg film-coated extended-release tablets (round, white-colored, bi-convex tablets debossed with OP on one side and 10 on the other)
- 15 mg film-coated extended-release tablets (round, gray-colored, bi-convex tablets debossed with OP on one side and 15 on the other)
- 20 mg film-coated extended-release tablets (round, pink-colored, bi-convex tablets debossed with OP on one side and 20 on the other)
- 30 mg film-coated extended-release tablets (round, brown-colored, bi-convex tablets debossed with OP on one side and 30 on the other)
- 40 mg film-coated extended-release tablets (round, yellow-colored, bi-convex tablets debossed with OP on one side and 40 on the other)
- 60 mg film-coated extended-release tablets (round, red-colored, bi-convex tablets debossed with OP on one side and 60 on the other)
- 80 mg film-coated extended-release tablets (round, green-colored, bi-convex tablets debossed with OP on one side and 80 on the other)

4 CONTRAINDICATIONS

OXYCONTIN is contraindicated in patients with:

- Significant respiratory depression [see Warnings and Precautions (5.2)]
- Acute or severe bronchial asthma in an unmonitored setting or in the absence of resuscitative equipment [see Warnings and Precautions (5.8)]
- Known or suspected gastrointestinal obstruction, including paralytic ileus [see Warnings and Precautions (5.13)]
- Hypersensitivity (e.g., anaphylaxis) to oxycodone [see Adverse Reactions (6.2)]

5 WARNINGS AND PRECAUTIONS

5.1 Addiction, Abuse, and Misuse

OXYCONTIN contains oxycodone, a Schedule II controlled substance. As an opioid, OXYCONTIN exposes users to the risks of addiction, abuse, and misuse.

Although the risk of addiction in any individual is unknown, it can occur in patients appropriately prescribed OXYCONTIN. Addiction can occur at recommended doses and if the drug is misused or abused. The risk of opioid-related overdose or overdose-related death is increased with higher opioid doses, and this risk persists over the course of therapy. In postmarketing studies, addiction, abuse, misuse, and fatal and non-fatal opioid overdose were observed in patients with long-term opioid use [see Adverse Reactions (6.2)].

Assess each patient's risk for opioid addiction, abuse, or misuse prior to prescribing OXYCONTIN, and reassess all patients receiving OXYCONTIN for the development of these behaviors and conditions. Risks are increased in patients with a personal or family history of substance abuse (including drug or alcohol abuse or addiction) or mental illness (e.g., major depression). The potential for these risks should not, however, prevent the proper management of pain in any given patient. Patients at increased risk may be prescribed opioids such as OXYCONTIN but use in such patients necessitates intensive counseling about the risks and proper use of OXYCONTIN along with frequent reevaluation for signs of addiction, abuse, and misuse. Consider recommending or prescribing an opioid overdose reversal agent for the emergency treatment of opioid overdose [see Dosage and Administration (2.2), Warnings and Precautions (5.2)].

Abuse or misuse of OXYCONTIN by crushing, chewing, snorting, or injecting the dissolved product will result in the uncontrolled delivery of oxycodone and can result in overdose and death [see Overdosage (10)].

Opioids are sought for nonmedical use and are subject to diversion from legitimate prescribed use. Consider these risks when prescribing or dispensing OXYCONTIN. Strategies to reduce these risks include prescribing the drug in the smallest appropriate quantity and advising the patient on careful storage of the drug during the course of treatment and the proper disposal of unused drug. Contact local state professional licensing board or state-controlled substances authority for information on how to prevent and detect abuse or diversion of this product.

5.2 Life-Threatening Respiratory Depression

Serious, life-threatening, or fatal respiratory depression has been reported with the use of opioids, even when used as recommended. Respiratory depression, if not immediately recognized and treated, may lead to respiratory arrest and death. Management of respiratory depression may include close observation, supportive measures, and use of opioid overdose reversal agents, depending on the patient's clinical status [see Overdosage (10)]. Carbon dioxide (CO2) retention from opioid-induced respiratory depression can exacerbate the sedating effects of opioids.

While serious, life-threatening, or fatal respiratory depression can occur at any time during the use of OXYCONTIN, the risk is greatest during the initiation of therapy or following a dosage increase.

To reduce the risk of respiratory depression, proper dosing and titration of OXYCONTIN are essential [see Dosage and Administration (2)]. Overestimating the OXYCONTIN dosage when converting patients from another opioid product can result in a fatal overdose with the first dose.

Accidental ingestion of even one dose of OXYCONTIN, especially by children, can result in respiratory depression and death due to an overdose of oxycodone.

Educate patients and caregivers on how to recognize respiratory depression and emphasize the importance of calling 911 or getting emergency medical help right away in the event of a known or suspected overdose.

Opioids can cause sleep-related breathing disorders including central sleep apnea (CSA) and sleep-related hypoxemia. Opioid use increases the risk of CSA in a dose-dependent fashion. In patients who present with CSA, consider decreasing the opioid dosage using best practices for opioid taper [see Dosage and Administration (2.9)].

Patient Access to an Opioid Overdose Reversal Agent for the Emergency Treatment of Opioid Overdose:

Inform patients and caregivers about opioid overdose reversal agents (e.g., naloxone, nalmefene). Discuss the importance of having access to an opioid overdose reversal agent, especially if the patient has risk factors for overdose (e.g., concomitant use of CNS depressants, a history of opioid use disorder, or prior opioid overdose) or if there are household members (including children) or other close contacts at risk for accidental ingestion or opioid overdose. The presence of risk factors for overdose should not prevent the management of pain in any patient [see Warnings and Precautions (5.1, 5.3)].

Discuss the options for obtaining an opioid overdose reversal agent (e.g., prescription, over-the-counter, or as part of a community-based program).

There are important differences among the opioid overdose reversal agents, such as route of administration, product strength, approved patient age range, and pharmacokinetics. Be familiar with these differences, as outlined in the approved labeling for those products, prior to recommending or prescribing such an agent.

Educate patients and caregivers on how to recognize respiratory depression, and how to use an opioid overdose reversal agent for the emergency treatment of opioid overdose. Emphasize the importance of calling 911 or getting emergency medical help, even if an opioid overdose reversal agent is administered [see Dosage and Administration (2.2), Warnings and Precautions (5.1, 5.3), Overdosage (10)].

5.3 Risks from Concomitant Use with Benzodiazepines or Other CNS Depressants

Profound sedation, respiratory depression, coma, and death may result from concomitant use of OXYCONTIN with benzodiazepines and/or other CNS depressants, including alcohol (e.g., non-benzodiazepine sedatives/hypnotics, anxiolytics, tranquilizers, muscle relaxants, general anesthetics, antipsychotics, gabapentinoids [gabapentin or pregabalin], and other opioids). Because of these risks, reserve concomitant prescribing of these drugs for use in patients for whom alternative treatment options are inadequate.

Observational studies have demonstrated that concomitant use of opioid analgesics and benzodiazepines increases the risk of drug-related mortality compared to use of opioid analgesics alone. Because of similar pharmacological properties, it is reasonable to expect similar risk with the concomitant use of other CNS depressant drugs with opioid analgesics [see Drug Interactions (7)].

If the decision is made to prescribe a benzodiazepine or other CNS depressant concomitantly with an opioid analgesic, prescribe the lowest effective dosages and minimum durations of concomitant use. In patients already receiving an opioid analgesic, prescribe a lower initial dose of the benzodiazepine or other CNS depressant than indicated in the absence of an opioid, and titrate based on clinical response. If an opioid analgesic is initiated in a patient already taking a benzodiazepine or other CNS depressant, prescribe a lower initial dose of the opioid analgesic, and titrate based on clinical response. Inform patients and caregivers of this potential interaction and educate them on the signs and symptoms of respiratory depression (including sedation).

If concomitant use is warranted, consider recommending or prescribing an opioid overdose reversal agent [see Dosage and Administration (2.2), Warnings and Precautions (5.2), Overdosage (10)].

Advise both patients and caregivers about the risks of respiratory depression and sedation when OXYCONTIN is used with benzodiazepines or other CNS depressants (including alcohol and illicit drugs). Advise patients not to drive or operate heavy machinery until the effects of concomitant use of the benzodiazepine or other CNS depressant have been determined. Screen patients for risk of substance use disorders, including opioid abuse and misuse, and warn them of the risk for overdose and death associated with the use of additional CNS depressants including alcohol and illicit drugs [see Drug Interactions (7)].

5.4 Neonatal Opioid Withdrawal Syndrome

Use of OXYCONTIN for an extended period of time during pregnancy can result in withdrawal in the neonate. Neonatal opioid withdrawal syndrome, unlike opioid withdrawal syndrome in adults, may be life-threatening if not recognized and treated, and requires management according to protocols developed by neonatology experts. Observe newborns for signs of neonatal opioid withdrawal syndrome and manage accordingly. Advise pregnant women using opioids for an extended period of time of the risk of neonatal opioid withdrawal syndrome and ensure that appropriate treatment will be available [see Use in Specific Populations (8.1)].

5.5 Opioid Analgesic Risk Evaluation and Mitigation Strategy (REMS)

To ensure that the benefits of opioid analgesics outweigh the risks of addiction, abuse, and misuse, the Food and Drug Administration (FDA) has required a Risk Evaluation and Mitigation Strategy (REMS) for these products. Under the requirements of the REMS, drug companies with approved opioid analgesic products must make REMS-compliant education programs available to healthcare providers. Healthcare providers are strongly encouraged to do all of the following:

- Complete a REMS-compliant education program offered by an accredited provider of continuing education (CE) or another education program that includes all the elements of the FDA Education Blueprint for Health Care Providers Involved in the Management or Support of Patients with Pain.
- Discuss the safe use, serious risks, and proper storage and disposal of opioid analgesics with patients and/or their caregivers every time these medicines are prescribed. The Patient Counseling Guide (PCG) can be obtained at this link:
  www.fda.gov/OpioidAnalgesicREMSPCG.
- Emphasize to patients and their caregivers the importance of reading the Medication Guide that they will receive from their pharmacist every time an opioid analgesic is dispensed to them.
- Consider using other tools to improve patient, household, and community safety, such as patient-prescriber agreements that reinforce patient-prescriber responsibilities.

To obtain further information on the opioid analgesic REMS and for a list of accredited REMS CME/CE, call 1-800-503-0784, or log on to www.opioidanalgesicrems.com. The FDA Blueprint can be found at www.fda.gov/OpioidAnalgesicREMSBlueprint.

5.6 Risks of Concomitant Use or Discontinuation of Cytochrome P450 3A4 Inhibitors and Inducers

Concomitant use of OXYCONTIN with a CYP3A4 inhibitor, such as macrolide antibiotics (e.g., erythromycin), azole-antifungal agents (e.g., ketoconazole), and protease inhibitors (e.g., ritonavir), may increase plasma concentrations of oxycodone and prolong opioid adverse reactions, which may cause potentially fatal respiratory depression [see Warnings and Precautions (5.2)], particularly when an inhibitor is added after a stable dose of OXYCONTIN is achieved. Similarly, discontinuation of a CYP3A4 inducer, such as rifampin, carbamazepine, and phenytoin, in OXYCONTIN-treated patients may increase oxycodone plasma concentrations and prolong opioid adverse reactions. When using OXYCONTIN with CYP3A4 inhibitors or discontinuing CYP3A4 inducers in OXYCONTIN-treated patients, evaluate patients at frequent intervals and consider dosage reduction of OXYCONTIN until stable drug effects are achieved [see Drug Interactions (7)].

Concomitant use of OXYCONTIN with CYP3A4 inducers or discontinuation of a CYP3A4 inhibitor could decrease oxycodone plasma concentrations, decrease opioid efficacy or, possibly, lead to a withdrawal syndrome in a patient who had developed physical dependence to oxycodone. When using OXYCONTIN with CYP3A4 inducers or discontinuing CYP3A4 inhibitors, evaluate patients at frequent intervals and consider increasing the opioid dosage if needed to maintain adequate analgesia or if symptoms of opioid withdrawal occur [see Drug Interactions (7)].

5.7 Opioid-Induced Hyperalgesia and Allodynia

Opioid-Induced Hyperalgesia (OIH) occurs when an opioid analgesic paradoxically causes an increase in pain, or an increase in sensitivity to pain. This condition differs from tolerance, which is the need for increasing doses of opioids to maintain a defined effect [see Dependence (9.3)]. Symptoms of OIH include (but may not be limited to) increased levels of pain upon opioid dosage increase, decreased levels of pain upon opioid dosage decrease, or pain from ordinarily non-painful stimuli (allodynia). These symptoms may suggest OIH only if there is no evidence of underlying disease progression, opioid tolerance, opioid withdrawal, or addictive behavior.

Cases of OIH have been reported, both with short-term and longer-term use of opioid analgesics. Though the mechanism of OIH is not fully understood, multiple biochemical pathways have been implicated. Medical literature suggests a strong biologic plausibility between opioid analgesics and OIH and allodynia. If a patient is suspected to be experiencing OIH, carefully consider appropriately decreasing the dose of the current opioid analgesic or opioid rotation (safely switching the patient to a different opioid moiety) [see Dosage and Administration (2.9), Warnings and Precautions (5.15)].

5.8 Life-Threatening Respiratory Depression in Patients with Chronic Pulmonary Disease or in Elderly, Cachectic, or Debilitated Patients

The use of OXYCONTIN in patients with acute or severe bronchial asthma in an unmonitored setting or in the absence of resuscitative equipment is contraindicated.

Patients with Chronic Pulmonary Disease: OXYCONTIN-treated patients with significant chronic obstructive pulmonary disease or cor pulmonale, and those with a substantially decreased respiratory reserve, hypoxia, hypercapnia, or pre-existing respiratory depression are at increased risk of decreased respiratory drive including apnea, even at recommended dosages of OXYCONTIN [see Warnings and Precautions (5.2)].

Elderly, Cachectic, or Debilitated Patients: Life-threatening respiratory depression is more likely to occur in elderly, cachectic, or debilitated patients because they may have altered pharmacokinetics or altered clearance compared to younger, healthier patients [see Warnings and Precautions (5.2)].

Regularly evaluate patients, particularly when initiating and titrating OXYCONTIN and when OXYCONTIN is given concomitantly with other drugs that depress respiration [see Warnings and Precautions (5.2, 5.3), Drug Interactions (7)]. Alternatively, consider the use of non-opioid analgesics in these patients.

5.9 Adrenal Insufficiency

Cases of adrenal insufficiency have been reported with opioid use, more often following greater than one month of use. Presentation of adrenal insufficiency may include non-specific symptoms and signs including nausea, vomiting, anorexia, fatigue, weakness, dizziness, and low blood pressure. If adrenal insufficiency is suspected, confirm the diagnosis with diagnostic testing as soon as possible. If adrenal insufficiency is diagnosed, treat with physiologic replacement doses of corticosteroids. Wean the patient off of the opioid to allow adrenal function to recover and continue corticosteroid treatment until adrenal function recovers. Other opioids may be tried as some cases reported use of a different opioid without recurrence of adrenal insufficiency. The information available does not identify any particular opioids as being more likely to be associated with adrenal insufficiency.

5.10 Severe Hypotension

OXYCONTIN may cause severe hypotension, including orthostatic hypotension and syncope in ambulatory patients. There is an increased risk in patients whose ability to maintain blood pressure has already been compromised by a reduced blood volume or concurrent administration of certain CNS depressant drugs (e.g., phenothiazines or general anesthetics) [see Drug Interactions (7)]. Regularly evaluate these patients for signs of hypotension after initiating or titrating the dosage of OXYCONTIN. In patients with circulatory shock, OXYCONTIN may cause vasodilation that can further reduce cardiac output and blood pressure. Avoid the use of OXYCONTIN in patients with circulatory shock.

5.11 Risks of Use in Patients with Increased Intracranial Pressure, Brain Tumors, Head Injury, or Impaired Consciousness

In patients who may be susceptible to the intracranial effects of CO2 retention (e.g., those with evidence of increased intracranial pressure or brain tumors), OXYCONTIN may reduce respiratory drive, and the resultant CO2 retention can further increase intracranial pressure. Monitor such patients for signs of sedation and respiratory depression, particularly when initiating therapy with OXYCONTIN.

Opioids may also obscure the clinical course in a patient with a head injury. Avoid the use of OXYCONTIN in patients with impaired consciousness or coma.

5.12 Difficulty in Swallowing and Risk for Obstruction in Patients at Risk for a Small Gastrointestinal Lumen

There have been post-marketing reports of difficulty in swallowing OXYCONTIN tablets. These reports included choking, gagging, regurgitation and tablets stuck in the throat. Instruct patients not to pre-soak, lick, or otherwise wet OXYCONTIN tablets prior to placing in the mouth, and to take one tablet at a time with enough water to ensure complete swallowing immediately after placing in the mouth.

There have been rare post-marketing reports of cases of intestinal obstruction, and exacerbation of diverticulitis, some of which have required medical intervention to remove the tablet. Patients with underlying GI disorders such as esophageal cancer or colon cancer with a small gastrointestinal lumen are at greater risk of developing these complications. Consider use of an alternative analgesic in patients who have difficulty swallowing and patients at risk for underlying GI disorders resulting in a small gastrointestinal lumen.

5.13 Risks of Gastrointestinal Complications

OXYCONTIN is contraindicated in patients with known or suspected gastrointestinal obstruction, including paralytic ileus.

The oxycodone in OXYCONTIN may cause spasm of the sphincter of Oddi. Opioids may cause increases in the serum amylase. Regularly evaluate patients with biliary tract disease, including acute pancreatitis, for worsening symptoms.

Cases of opioid-induced esophageal dysfunction (OIED) have been reported in patients taking opioids. The risk of OIED may increase as the dose and/or duration of opioids increases. Regularly evaluate patients for signs and symptoms of OIED (e.g., dysphagia, regurgitation, non-cardiac chest pain) and, if necessary, adjust opioid therapy as clinically appropriate [see Clinical Pharmacology (12.2)].

5.14 Increased Risk of Seizures in Patients with Seizure Disorders

The oxycodone in OXYCONTIN may increase the frequency of seizures in patients with seizure disorders and may increase the risk of seizures occurring in other clinical settings associated with seizures. Regularly evaluate patients with a history of seizure disorders for worsened seizure control during OXYCONTIN therapy.

5.15 Withdrawal

Do not rapidly reduce or abruptly discontinue OXYCONTIN in a patient physically dependent on opioids. When discontinuing OXYCONTIN in a physically-dependent patient, gradually taper the dosage. Rapid tapering of oxycodone in a patient physically dependent on opioids may lead to a withdrawal syndrome and return of pain [see Dosage and Administration (2.9), Drug Abuse and Dependence (9.3)].

Additionally, avoid the use of mixed agonist/antagonist (e.g., pentazocine, nalbuphine, and butorphanol) or partial agonist (e.g., buprenorphine) analgesics in patients who are receiving a full opioid agonist analgesic, including OXYCONTIN. In these patients, mixed agonist/antagonist and partial agonist analgesics may reduce the analgesic effect and/or may precipitate withdrawal symptoms.

5.16 Risks of Driving and Operating Machinery

OXYCONTIN may impair the mental or physical abilities needed to perform potentially hazardous activities such as driving a car or operating machinery. Warn patients not to drive or operate dangerous machinery unless they are tolerant to the effects of OXYCONTIN and know how they will react to the medication.

5.17 Laboratory Monitoring

Not every urine drug test for "opioids" or "opiates" detects oxycodone reliably, especially those designed for in-office use. Further, many laboratories will report urine drug concentrations below a specified "cut-off" value as "negative". Therefore, if urine testing for oxycodone is considered in the clinical management of an individual patient, ensure that the sensitivity and specificity of the assay is appropriate, and consider the limitations of the testing used when interpreting results.

6 ADVERSE REACTIONS

The following serious adverse reactions are described elsewhere in the labeling:

- Addiction, Abuse, and Misuse [see Warnings and Precautions (5.1)]
- Life-Threatening Respiratory Depression [see Warnings and Precautions (5.2)]
- Interactions With Benzodiazepines and Other CNS Depressants [see Warnings and Precautions (5.3)]
- Neonatal Opioid Withdrawal Syndrome [see Warnings and Precautions (5.4)]
- Opioid-Induced Hyperalgesia and Allodynia [see Warnings and Precautions (5.7)]
- Adrenal Insufficiency [see Warnings and Precautions (5.9)]
- Severe Hypotension [see Warnings and Precautions (5.10)]
- Gastrointestinal Adverse Reactions [see Warnings and Precautions (5.12, 5.13)]
- Seizures [see Warnings and Precautions (5.14)]
- Withdrawal [see Warnings and Precautions (5.15)]

6.1 Clinical Trial Experience

Adult Clinical Trial Experience

Because clinical trials are conducted under widely varying conditions, adverse reaction rates observed in the clinical trials of a drug cannot be directly compared to rates in the clinical trials of another drug and may not reflect the rates observed in practice.

The safety of OXYCONTIN was evaluated in double-blind clinical trials involving 713 patients with moderate to severe pain of various etiologies. In open-label studies of cancer pain, 187 patients received OXYCONTIN in total daily doses ranging from 20 mg to 640 mg per day. The average total daily dose was approximately 105 mg per day.

OXYCONTIN may increase the risk of serious adverse reactions such as those observed with other opioid analgesics, including respiratory depression, apnea, respiratory arrest, circulatory depression, hypotension, or shock [see Overdosage (10)].

The most common adverse reactions (>5%) reported by patients in clinical trials comparing OXYCONTIN with placebo are shown in Table 2 below:

TABLE 2: Common Adverse Reactions (>5%)
Adverse Reaction | OXYCONTIN (n=227) | Placebo (n=45)
Adverse Reaction | (%) | (%)
Constipation | (23) | (7)
Nausea | (23) | (11)
Somnolence | (23) | (4)
Dizziness | (13) | (9)
Pruritus | (13) | (2)
Vomiting | (12) | (7)
Headache | (7) | (7)
Dry Mouth | (6) | (2)
Asthenia | (6) | -
Sweating | (5) | (2)

In clinical trials, the following adverse reactions were reported in patients treated with OXYCONTIN with an incidence between 1% and 5%:

Gastrointestinal disorders: abdominal pain, diarrhea, dyspepsia, gastritis

General disorders and administration site conditions: chills, fever

Metabolism and nutrition disorders: anorexia

Musculoskeletal and connective tissue disorders: twitching

Psychiatric disorders: abnormal dreams, anxiety, confusion, dysphoria, euphoria, insomnia, nervousness, thought abnormalities

Respiratory, thoracic and mediastinal disorders: dyspnea, hiccups

Skin and subcutaneous tissue disorders: rash

Vascular disorders: postural hypotension

The following adverse reactions occurred in less than 1% of patients involved in clinical trials:

Blood and lymphatic system disorders: lymphadenopathy

Ear and labyrinth disorders: tinnitus

Eye disorders: abnormal vision

Gastrointestinal disorders: dysphagia, eructation, flatulence, gastrointestinal disorder, increased appetite, stomatitis

General disorders and administration site conditions: withdrawal syndrome (with and without seizures), edema, peripheral edema, thirst, malaise, chest pain, facial edema

Injury, poisoning and procedural complications: accidental injury

Investigations: ST depression

Metabolism and nutrition disorders: dehydration

Nervous system disorders: syncope, migraine, abnormal gait, amnesia, hyperkinesia, hypoesthesia, hypotonia, paresthesia, speech disorder, stupor, tremor, vertigo, taste perversion

Psychiatric disorders: depression, agitation, depersonalization, emotional lability, hallucination

Renal and urinary disorders: dysuria, hematuria, polyuria, urinary retention

Reproductive system and breast disorders: impotence

Respiratory, thoracic and mediastinal disorders: cough increased, voice alteration

Skin and subcutaneous tissue disorders: dry skin, exfoliative dermatitis

Clinical Trial Experience in Pediatric Patients 11 Years and Older

The safety of OXYCONTIN has been evaluated in one clinical trial with 140 patients 11 to 16 years of age. The median duration of treatment was approximately three weeks. The most frequently reported adverse events were vomiting, nausea, headache, pyrexia, and constipation.

Table 3 includes a summary of the incidence of treatment emergent adverse events reported in ≥5% of patients.

Table 3: Incidence of Adverse Reactions Reported in ≥ 5.0% Patients 11 to 16 Years
System Organ Class Preferred Term | 11 to 16 Years (N=140) n (%)
Any Adverse Event >= 5% | 71 (51)
GASTROINTESTINAL DISORDERS | 56 (40)
Vomiting | 30 (21)
Nausea | 21 (15)
Constipation | 13 (9)
Diarrhea | 8 (6)
GENERAL DISORDERS AND ADMINISTRATION SITE CONDITIONS | 32 (23)
Pyrexia | 15 (11)
METABOLISM AND NUTRITION DISORDERS | 9 (6)
Decreased appetite | 7 (5)
NERVOUS SYSTEM DISORDERS | 37 (26)
Headache | 20 (14)
Dizziness | 12 (9)
SKIN AND SUBCUTANEOUS TISSUE DISORDERS | 23 (16)
Pruritus | 8 (6)

The following adverse reactions occurred in a clinical trial of OXYCONTIN in patients 11 to 16 years of age with an incidence between ≥1.0% and < 5.0%. Events are listed within each System/Organ Class.

Blood and lymphatic system disorders: febrile neutropenia, neutropenia

Cardiac disorders: tachycardia

Gastrointestinal disorders: abdominal pain, gastroesophageal reflux disease

General disorders and administration site conditions: fatigue, pain, chills, asthenia

Injury, poisoning, and procedural complications: procedural pain, seroma

Investigations: oxygen saturation decreased, alanine aminotransferase increased, hemoglobin decreased, platelet count decreased, neutrophil count decreased, red blood cell count decreased, weight decreased

Metabolic and nutrition disorders: hypochloremia, hyponatremia

Musculoskeletal and connective tissue disorders: pain in extremity, musculoskeletal pain

Nervous system disorders: somnolence, hypoesthesia, lethargy, paresthesia

Psychiatric disorders: insomnia, anxiety, depression, agitation

Renal and urinary disorders: dysuria, urinary retention

Respiratory, thoracic, and mediastinal disorders: oropharyngeal pain

Skin and subcutaneous tissue disorders: hyperhidrosis, rash

6.2 Postmarketing Experience

The following adverse reactions have been identified during post-approval use of extended-release oxycodone. Because these reactions are reported voluntarily from a population of uncertain size, it is not always possible to reliably estimate their frequency or establish a causal relationship to drug exposure.

Abuse, addiction, aggression, amenorrhea, cholestasis, completed suicide, death, dental caries, increased hepatic enzymes, hyperalgesia, hypogonadism, hyponatremia, ileus, intentional overdose, mood altered, muscular hypertonia, overdose, palpitations (in the context of withdrawal), seizures, suicidal attempt, suicidal ideation, syndrome of inappropriate antidiuretic hormone secretion, and urticaria.

In addition to the events listed above, the following have also been reported, potentially due to the swelling and hydrogelling property of the tablet: choking, gagging, regurgitation, tablets stuck in the throat and difficulty swallowing the tablet.

Serotonin syndrome: Cases of serotonin syndrome, a potentially life-threatening condition, have been reported during concomitant use of opioids with serotonergic drugs.

Adrenal insufficiency: Cases of adrenal insufficiency have been reported with opioid use, more often following greater than one month of use.

Anaphylaxis: Anaphylaxis has been reported with ingredients contained in OXYCONTIN.

Androgen deficiency: Cases of androgen deficiency have occurred with use of opioids for an extended period of time [see Clinical Pharmacology (12.2)].

Hyperalgesia and Allodynia: Cases of hyperalgesia and allodynia have been reported with opioid therapy of any duration [see Warnings and Precautions (5.7)].

Hypoglycemia: Cases of hypoglycemia have been reported in patients taking opioids. Most reports were in patients with at least one predisposing risk factor (e.g., diabetes).

Opioid-induced esophageal dysfunction (OIED): Cases of OIED have been reported in patients taking opioids and may occur more frequently in patients taking higher doses of opioids, and/or in patients taking opioids longer term [see Warnings and Precautions (5.13)].

Adverse Reactions from Observational Studies

A prospective, observational cohort study estimated the risks of addiction, abuse, and misuse in patients initiating long-term use of Schedule II opioid analgesics between 2017 and 2021. Study participants included in one or more analyses had been enrolled in selected insurance plans or health systems for at least one year, were free of at least one outcome at baseline, completed a minimum number of follow-up assessments, and either: 1) filled multiple extended-release/long-acting opioid analgesic prescriptions during a 90-day period (n=978); or 2) filled any Schedule II opioid analgesic prescriptions covering at least 70 of 90 days (n=1,244). Those included also had no dispensing of the qualifying opioids in the previous 6 months.

Over 12 months:

- approximately 1% to 6% of participants across the two cohorts newly met criteria for addiction, as assessed with two validated interview-based measures of moderate-to-severe opioid use disorder based on Diagnostic and Statistical Manual of Mental Disorders, Fifth Edition (DSM-5) criteria, and
- approximately 9% and 22% of participants across the two cohorts newly met criteria for prescription opioid abuse and misuse [defined in Drug Abuse and Dependence (9.2)], respectively, as measured with a validated self-reported instrument.

A retrospective, observational cohort study estimated the risk of opioid-involved overdose or opioid overdose-related death in patients with new long-term use of Schedule II opioid analgesics from 2006 through 2016 (n=220,249). Included patients had been enrolled in either one of two commercial insurance programs, one managed care program, or one Medicaid program for at least 9 months. New long-term use was defined as having Schedule II opioid analgesic prescriptions covering at least 70 days' supply over the 3 months prior to study entry and none during the preceding 6 months. Patients were excluded if they had an opioid-involved overdose in the 9 months prior to study entry. Overdose was measured using a validated medical code-based algorithm with linkage to the National Death Index database. The 5-year cumulative incidence estimates for opioid-involved overdose or opioid overdose-related death ranged from approximately 1.5% to 4% across study sites, counting only the first event during follow-up. Approximately 17% of first opioid overdoses observed over the entire study period (5-11 years, depending on the study site) were fatal. Higher baseline opioid dose was the strongest and most consistent predictor of opioid-involved overdose or opioid overdose-related death.

Study exclusion criteria may have selected patients at lower risk of overdose, and substantial loss to follow-up (approximately 80%) also may have biased estimates.

The risk estimates from the studies described above may not be generalizable to all patients receiving opioid analgesics, such as those with exposures shorter or longer than the duration evaluated in the studies.

7 DRUG INTERACTIONS

Table 4 includes clinically significant drug interactions with OXYCONTIN.

Table 4: Clinically Significant Drug Interactions with OXYCONTIN
Inhibitors of CYP3A4 and CYP2D6
Clinical Impact: | The concomitant use of OXYCONTIN and CYP3A4 inhibitors can increase the plasma concentration of oxycodone, resulting in increased or prolonged opioid effects. These effects could be more pronounced with concomitant use of OXYCONTIN and CYP2D6 and CYP3A4 inhibitors, particularly when an inhibitor is added after a stable dose of OXYCONTIN is achieved [see Warnings and Precautions (5.6)]. After stopping a CYP3A4 inhibitor, as the effects of the inhibitor decline, the oxycodone plasma concentration will decrease [see Clinical Pharmacology (12.3)], resulting in decreased opioid efficacy or a withdrawal syndrome in patients who had developed physical dependence to oxycodone.
Intervention: | If concomitant use is necessary, consider dosage reduction of OXYCONTIN until stable drug effects are achieved. Evaluate patients at frequent intervals for respiratory depression and sedation. If a CYP3A4 inhibitor is discontinued, consider increasing the OXYCONTIN dosage until stable drug effects are achieved. Assess for signs of opioid withdrawal.
Examples: | Macrolide antibiotics (e.g., erythromycin), azole-antifungal agents (e.g., ketoconazole), protease inhibitors (e.g., ritonavir)
CYP3A4 Inducers
Clinical Impact: | The concomitant use of OXYCONTIN and CYP3A4 inducers can decrease the plasma concentration of oxycodone [see Clinical Pharmacology (12.3)], resulting in decreased efficacy or onset of a withdrawal syndrome in patients who have developed physical dependence to oxycodone [see Warnings and Precautions (5.6)]. After stopping a CYP3A4 inducer, as the effects of the inducer decline, the oxycodone plasma concentration will increase [see Clinical Pharmacology (12.3)], which could increase or prolong both the therapeutic effects and adverse reactions and may cause serious respiratory depression.
Intervention: | If concomitant use is necessary, consider increasing the OXYCONTIN dosage until stable drug effects are achieved. Evaluate for signs of opioid withdrawal. If a CYP3A4 inducer is discontinued, consider OXYCONTIN dosage reduction and evaluate patients at frequent intervals for signs of respiratory depression and sedation.
Examples: | Rifampin, carbamazepine, phenytoin
Benzodiazepines and Other Central Nervous System (CNS) Depressants
Clinical Impact: | Due to additive pharmacologic effect, the concomitant use of benzodiazepines or other CNS depressants, including alcohol, can increase the risk of hypotension, respiratory depression, profound sedation, coma, and death [see Warnings and Precautions (5.3)].
Intervention: | Reserve concomitant prescribing of these drugs for use in patients for whom alternative treatment options are inadequate. Limit dosages and durations to the minimum required. Inform patients and caregivers of this potential interaction and educate them on the signs and symptoms of respiratory depression (including sedation). If concomitant use is warranted, consider recommending or prescribing an opioid overdose reversal agent [see Dosage and Administration (2.2, 2.6), Warnings and Precautions (5.2, 5.3)].
Examples: | Benzodiazepines and other sedatives/hypnotics, anxiolytics, tranquilizers, muscle relaxants, general anesthetics, antipsychotics, gabapentinoids (gabapentin or pregabalin), other opioids, alcohol.
Serotonergic Drugs
Clinical Impact: | The concomitant use of opioids with other drugs that affect the serotonergic neurotransmitter system has resulted in serotonin syndrome.
Intervention: | If concomitant use is warranted, frequently evaluate the patient, particularly during treatment initiation and dose adjustment. Discontinue OXYCONTIN if serotonin syndrome is suspected.
Examples: | Selective serotonin reuptake inhibitors (SSRIs), serotonin and norepinephrine reuptake inhibitors (SNRIs), tricyclic antidepressants (TCAs), triptans, 5-HT3 receptor antagonists, drugs that affect the serotonin neurotransmitter system (e.g., mirtazapine, trazodone, tramadol), certain muscle relaxants (i.e., cyclobenzaprine, metaxalone), monoamine oxidase inhibitors (those intended to treat psychiatric disorders and also others, such as linezolid and intravenous methylene blue).
Monoamine Oxidase Inhibitors (MAOIs)
Clinical Impact: | MAOI interactions with opioids may manifest as serotonin syndrome or opioid toxicity (e.g., respiratory depression, coma) [see Warnings and Precautions (5.2)].
Intervention: | The use of OXYCONTIN is not recommended for patients taking MAOIs or within 14 days of stopping such treatment.
Examples: | phenelzine, tranylcypromine, linezolid
Mixed Agonist/Antagonist and Partial Agonist Opioid Analgesics
Clinical Impact: | May reduce the analgesic effect of OXYCONTIN and/or precipitate withdrawal symptoms.
Intervention: | Avoid concomitant use.
Examples: | butorphanol, nalbuphine, pentazocine, buprenorphine
Muscle Relaxants
Clinical Impact: | Oxycodone may enhance the neuromuscular blocking action of skeletal muscle relaxants and produce an increased degree of respiratory depression.
Intervention: | Because respiratory depression may be greater than otherwise expected, decrease the dosage of OXYCONTIN and/or the muscle relaxant as necessary. Due to the risk of respiratory depression with concomitant use of skeletal muscle relaxants and opioids, consider recommending or prescribing an opioid overdose reversal agent [see Dosage and Administration (2.2), Warnings and Precautions (5.2, 5.3)].
Examples: | Cyclobenzaprine, metaxalone
Diuretics
Clinical Impact: | Opioids can reduce the efficacy of diuretics by inducing the release of antidiuretic hormone.
Intervention: | Evaluate patients for signs of diminished diuresis and/or effects on blood pressure and increase the dosage of the diuretic as needed.
Anticholinergic Drugs
Clinical Impact: | The concomitant use of anticholinergic drugs may increase risk of urinary retention and/or severe constipation, which may lead to paralytic ileus.
Intervention: | Evaluate patients for signs of urinary retention or reduced gastric motility when OXYCONTIN is used concomitantly with anticholinergic drugs.

8 USE IN SPECIFIC POPULATIONS

8.1 Pregnancy

Risk Summary

Use of opioid analgesics for an extended period of time during pregnancy may cause neonatal opioid withdrawal syndrome [see Warnings and Precautions (5.4)]. There are no available data with OXYCONTIN in pregnant women to inform a drug-associated risk for major birth defects and miscarriage. In animal reproduction studies, there was no embryo-fetal toxicity when oxycodone hydrochloride was orally administered to rats and rabbits, during the period of organogenesis, at doses 1.3 to 40 times the adult human dose of 60 mg/day, respectively. In a pre- and postnatal toxicity study, when oxycodone was orally administered to rats, there was transiently decreased pup body weight during lactation and the early post-weaning period at the dose equivalent to an adult dose of 60 mg/day. In several published studies, treatment of pregnant rats with oxycodone hydrochloride at clinically relevant doses and below resulted in neurobehavioral effects in offspring [see Data]. Based on animal data, advise pregnant women of the potential risk to a fetus.

The background risk of major birth defects and miscarriage for the indicated population is unknown. All pregnancies have a background risk of birth defect, loss, or other adverse outcomes. In the U.S. general population, the estimated background risk of major birth defects and miscarriage in clinically recognized pregnancies is 2 to 4% and 15 to 20%, respectively.

Clinical Considerations

Fetal/Neonatal Adverse Reactions

Use of opioid analgesics for an extended period of time during pregnancy for medical or nonmedical purposes can result in physical dependence in the neonate and neonatal opioid withdrawal syndrome shortly after birth.

Neonatal opioid withdrawal syndrome presents as irritability, hyperactivity and abnormal sleep pattern, high pitched cry, tremor, vomiting, diarrhea, and failure to gain weight. The onset, duration, and severity of neonatal opioid withdrawal syndrome vary based on the specific opioid used, duration of use, timing and amount of last maternal use, and rate of elimination of the drug by the newborn. Observe newborns for symptoms of neonatal opioid withdrawal syndrome and manage accordingly [see Warnings and Precautions (5.4)].

Labor or Delivery

Opioids cross the placenta and may produce respiratory depression and psycho-physiologic effects in neonates. An opioid overdose reversal agent, such as naloxone or nalmefene, must be available for reversal of opioid-induced respiratory depression in the neonate. OXYCONTIN is not recommended for use in women immediately prior to labor, when use of shorter-acting analgesics or other analgesic techniques are more appropriate. Opioid analgesics, including OXYCONTIN, can prolong labor through actions which temporarily reduce the strength, duration, and frequency of uterine contractions. However, this effect is not consistent and may be offset by an increased rate of cervical dilatation, which tends to shorten labor. Monitor neonates exposed to opioid analgesics during labor for signs of excess sedation and respiratory depression.

Data

Animal Data

Pregnant rats were treated with 0.5, 2, 4, and 8 mg/kg oxycodone hydrochloride (0.08, 0.3, 0.7, and 1.3 times the human daily dose of 60 mg/day, respectively based on a mg/m^2 basis) during the period of organogenesis. Oxycodone did not cause adverse effects to the fetus at exposures up to 1.3 times the human dose of 60 mg/day. The high dose produced maternal toxicity characterized by excessive gnawing on forelimbs and decreased body weight gain.

Pregnant rabbits were treated with 1, 5, 25, and 125 mg/kg oxycodone hydrochloride (0.3, 2, 8, and 40 times the human daily dose of 60 mg/day, respectively, based on a mg/m^2 basis) during the period of organogenesis. Oxycodone did not cause adverse effects to the fetus at exposures up to 40 times the human dose of 60 mg/day. The 25 mg/kg and 125 mg/kg doses high doses produced maternal toxicity characterized by decreased food consumption and body weight gain.

Pregnant rats were treated with 0.5, 2, and 6 mg/kg oxycodone hydrochloride (0.08, 0.32, and 1 times the human daily dose of 60 mg/kg, respectively, based on a mg/m^2 basis) during the period of organogenesis through lactation. Decreased body weight was found during lactation and the early post-weaning phase in pups nursed by mothers given the highest dose used (6 mg/kg/day, equivalent to an adult human dose of 60 mg/day, on a mg/m^2 basis). However, body weight of these pups recovered.

In published studies, offspring of pregnant rats administered oxycodone hydrochloride during gestation have been reported to exhibit neurobehavioral effects including altered stress responses and increased anxiety-like behavior (2 mg/kg/day IV from Gestation Day 8 to 21 and Postnatal Day 1, 3, and 5; 0.3 times an adult human oral dose of 60 mg/day on a mg/m^2 basis), and altered learning and memory (15 mg/kg/day orally from breeding through parturition; 2.4 times an adult human oral dose of 60 mg/day on a mg/m^2 basis).

8.2 Lactation

Oxycodone is present in breast milk. Published lactation studies report variable concentrations of oxycodone in breast milk with administration of immediate-release oxycodone to nursing mothers in the early postpartum period. The lactation studies did not assess breastfed infants for potential adverse reactions. Lactation studies have not been conducted with extended–release oxycodone, including OXYCONTIN, and no information is available on the effects of the drug on the breastfed infant or the effects of the drug on milk production. Because of the potential for serious adverse reactions, including excess sedation and respiratory depression in a breastfed infant, advise patients that breastfeeding is not recommended during treatment with OXYCONTIN.

Clinical Considerations

Monitor infants exposed to OXYCONTIN through breast milk for excess sedation and respiratory depression. Withdrawal symptoms can occur in breast-fed infants when maternal administration of an opioid analgesic is stopped, or when breast-feeding is stopped.

8.3 Females and Males of Reproductive Potential

Infertility

Use of opioids for an extended period of time may cause reduced fertility in females and males of reproductive potential. It is not known whether these effects on fertility are reversible [see Adverse Reactions (6.2), Clinical Pharmacology (12.2), Nonclinical Toxicology (13.1)].

8.4 Pediatric Use

The safety and efficacy of OXYCONTIN have been established in pediatric patients ages 11 to 16 years. Use of OXYCONTIN is supported by evidence from adequate and well-controlled trials with OXYCONTIN in adults as well as an open-label study in pediatric patients ages 6 to 16 years. However, there were insufficient numbers of patients less than 11 years of age enrolled in this study to establish the safety of the product in this age group.

The safety of OXYCONTIN in pediatric patients was evaluated in 155 patients previously receiving and tolerating opioids for at least 5 consecutive days with a minimum of 20 mg per day of oxycodone or its equivalent on the two days immediately preceding dosing with OXYCONTIN. Patients were started on a total daily dose ranging between 20 mg and 100 mg depending on prior opioid dose.

The most frequent adverse events observed in pediatric patients were vomiting, nausea, headache, pyrexia, and constipation [see Dosage and Administration (2.4), Adverse Reactions (6.1), Clinical Pharmacology (12.3), Clinical Studies (14)].

8.5 Geriatric Use

In controlled pharmacokinetic studies in elderly subjects (greater than 65 years) the clearance of oxycodone was slightly reduced. Compared to young adults, the plasma concentrations of oxycodone were increased approximately 15% [see Clinical Pharmacology (12.3)]. Of the total number of subjects (445) in clinical studies of oxycodone hydrochloride controlled-release tablets, 148 (33.3%) were age 65 and older (including those age 75 and older) while 40 (9.0%) were age 75 and older. In clinical trials with appropriate initiation of therapy and dose titration, no untoward or unexpected adverse reactions were seen in the elderly patients who received oxycodone hydrochloride controlled-release tablets. Thus, the usual doses and dosing intervals may be appropriate for elderly patients. However, a dosage reduction in debilitated, non-opioid-tolerant patients is recommended [see Dosage and Administration (2.7)].

Respiratory depression is the chief risk for elderly patients treated with opioids, and has occurred after large initial doses were administered to patients who are not opioid-tolerant or when opioids were co-administered with other agents that depress respiration. Titrate the dosage of OXYCONTIN slowly in geriatric patients and frequently reevaluate the patient for signs of central nervous system and respiratory depression [see Warnings and Precautions (5.8)].

Oxycodone is known to be substantially excreted by the kidney, and the risk of adverse reactions to this drug may be greater in patients with impaired renal function. Because elderly patients are more likely to have decreased renal function, care should be taken in dose selection, and it may be useful to regularly evaluate renal function.

8.6 Hepatic Impairment

A study of OXYCONTIN in patients with hepatic impairment demonstrated greater plasma concentrations than those seen at equivalent doses in persons with normal hepatic function [see Clinical Pharmacology (12.3)]. Therefore, a dosage reduction is recommended for these patients [see Dosage and Administration (2.8)]. Regularly evaluate closely for signs of respiratory depression, sedation, and hypotension.

8.7 Renal Impairment

In patients with renal impairment, as evidenced by decreased creatinine clearance (<60 mL/min), the concentrations of oxycodone in the plasma are approximately 50% higher than in subjects with normal renal function [see Clinical Pharmacology (12.3)]. Follow a conservative approach to dose initiation and adjust according to the clinical situation.

8.8 Sex Differences

In pharmacokinetic studies with OXYCONTIN, opioid-naïve females demonstrate up to 25% higher average plasma concentrations and greater frequency of typical opioid adverse events than males, even after adjustment for body weight. The clinical relevance of a difference of this magnitude is low for a drug intended for chronic usage at individualized dosages, and there was no male/female difference detected for efficacy or adverse events in clinical trials.

9 DRUG ABUSE AND DEPENDENCE

9.1 Controlled Substance

OXYCONTIN contains oxycodone, a Schedule II controlled substance.

9.2 Abuse

OXYCONTIN contains oxycodone, a substance with high potential for misuse and abuse, which can lead to the development of substance use disorder, including addiction [see Warnings and Precautions (5.1)].

Misuse is the intentional use, for therapeutic purposes, of a drug by an individual in a way other than prescribed by a healthcare provider or for whom it was not prescribed.

Abuse is the intentional, non-therapeutic use of a drug, even once, for its desirable psychological or physiological effects.

Drug addiction is a cluster of behavioral, cognitive, and physiological phenomena that may include a strong desire to take the drug, difficulties in controlling drug use (e.g., continuing drug use despite harmful consequences, giving a higher priority to drug use than other activities and obligations), and possible tolerance or physical dependence.

Misuse and abuse of OXYCONTIN increases the risk of overdose, which may lead to central nervous system and respiratory depression, hypotension, seizures, and death. The risk is increased with concurrent abuse of OXYCONTIN with alcohol and/or other CNS depressants. Abuse of and addiction to opioids in some individuals may not be accompanied by concurrent tolerance and symptoms of physical dependence. In addition, abuse of opioids can occur in the absence of addiction.

All patients treated with opioids require careful and frequent reevaluation for signs of misuse, abuse, and addiction, because use of opioid analgesic products carries the risk of addiction even under appropriate medical use. Patients at high risk of OXYCONTIN abuse include those with a history of prolonged use of any opioid, including products containing oxycodone, those with a history of drug or alcohol abuse, or those who use OXYCONTIN in combination with other abused drugs.

"Drug-seeking" behavior is very common in persons with substance use disorders. Drug-seeking tactics include emergency calls or visits near the end of office hours, refusal to undergo appropriate examination, testing, or referral, repeated "loss" of prescriptions, tampering with prescriptions, and reluctance to provide prior medical records or contact information for other treating healthcare provider(s). "Doctor shopping" (visiting multiple prescribers to obtain additional prescriptions) is common among people who abuse drugs and people with substance use disorder. Preoccupation with achieving adequate pain relief can be appropriate behavior in a patient with inadequate pain control.

OXYCONTIN, like other opioids, can be diverted for nonmedical use into illicit channels of distribution. Careful record-keeping of prescribing information, including quantity, frequency, and renewal requests, as required by state and federal law, is strongly advised.

Proper assessment of the patient, proper prescribing practices, periodic reevaluation of therapy, and proper dispensing and storage are appropriate measures that help to limit abuse of opioid drugs.

Risks Specific to Abuse of OXYCONTIN

Abuse of OXYCONTIN poses a risk of overdose and death. This risk is increased with concurrent abuse of OXYCONTIN with alcohol and/or other CNS depressants [see Warnings and Precautions (5.1, 5.3), Drug Interactions (7)].

Taking cut, broken, chewed, crushed, or dissolved OXYCONTIN enhances drug release and increases the risk of overdose and death.

OXYCONTIN is approved for oral use only.

With parenteral abuse, the inactive ingredients in OXYCONTIN can be expected to result in local tissue necrosis, infection, pulmonary granulomas, increased risk of endocarditis, valvular heart injury, embolism, and death.

Cases of thrombotic microangiopathy (a condition characterized clinically by thrombocytopenia, microangiopathic hemolytic anemia) associated with parenteral abuse have been reported.

Parenteral drug abuse is commonly associated with transmission of infectious diseases such as hepatitis and HIV.

Abuse Deterrence Studies

OXYCONTIN is formulated with inactive ingredients intended to make the tablet more difficult to manipulate for misuse and abuse. For the purposes of describing the results of studies of the abuse-deterrent characteristics of OXYCONTIN resulting from a change in formulation, in this section, the original formulation of OXYCONTIN, which is no longer marketed, will be referred to as "original OxyContin" and the reformulated, currently marketed product will be referred to as "OXYCONTIN."

In Vitro Testing

In vitro physical and chemical tablet manipulation studies were performed to evaluate the success of different extraction methods in defeating the extended-release formulation. Results support that, relative to original OxyContin, there is an increase in the ability of OXYCONTIN to resist crushing, breaking, and dissolution using a variety of tools and solvents. The results of these studies also support this finding for OXYCONTIN relative to an immediate-release oxycodone. When subjected to an aqueous environment, OXYCONTIN gradually forms a viscous hydrogel (i.e., a gelatinous mass) that resists passage through a needle.

Clinical Studies

In a randomized, double-blind, placebo-controlled 5-period crossover pharmacodynamic study, 30 recreational opioid users with a history of intranasal drug abuse received intranasally administered active and placebo drug treatments. The five treatment arms were finely crushed OXYCONTIN 30 mg tablets, coarsely crushed OXYCONTIN 30 mg tablets, finely crushed original OxyContin 30 mg tablets, powdered oxycodone HCl 30 mg, and placebo. Data for finely crushed OXYCONTIN, finely crushed original OxyContin, and powdered oxycodone HCl are described below.

Drug liking was measured on a bipolar drug liking scale of 0 to 100 where 50 represents a neutral response of neither liking nor disliking, 0 represents maximum disliking and 100 represents maximum liking. Response to whether the subject would take the study drug again was also measured on a bipolar scale of 0 to 100 where 50 represents a neutral response, 0 represents the strongest negative response ("definitely would not take drug again") and 100 represents the strongest positive response ("definitely would take drug again").

Twenty-seven of the subjects completed the study. Incomplete dosing due to granules falling from the subjects' nostrils occurred in 34% (n = 10) of subjects with finely crushed OXYCONTIN, compared with 7% (n = 2) of subjects with finely crushed original OxyContin and no subjects with powdered oxycodone HCl.

The intranasal administration of finely crushed OXYCONTIN was associated with a numerically lower mean and median drug liking score and a lower mean and median score for take drug again, compared to finely crushed original OxyContin or powdered oxycodone HCl as summarized in Table 5.

Table 5: Summary of Maximum Drug Liking (Emax) Data Following Intranasal Administration
VAS Scale (100 mm) [Bipolar scales (0 = maximum negative response, 50 = neutral response, 100 = maximum positive response)] |  | OXYCONTIN (finely crushed) | Original OxyContin (finely crushed) | Oxycodone HCl (powdered)
Drug Liking | Mean (SE) | 80.4 (3.9) | 94.0 (2.7) | 89.3 (3.1)
Drug Liking | Median (Range) | 88 (36-100) | 100 (51-100) | 100 (50-100)
Take Drug Again | Mean (SE) | 64.0 (7.1) | 89.6 (3.9) | 86.6 (4.4)
Take Drug Again | Median (Range) | 78 (0-100) | 100 (20-100) | 100 (0-100)

Figure 1 demonstrates a comparison of drug liking for finely crushed OXYCONTIN compared to powdered oxycodone HCl in subjects who received both treatments. The Y-axis represents the percent of subjects attaining a percent reduction in drug liking for OXYCONTIN vs. oxycodone HCl powder greater than or equal to the value on the X-axis. Approximately 44% (n = 12) had no reduction in liking with OXYCONTIN relative to oxycodone HCl. Approximately 56% (n = 15) of subjects had some reduction in drug liking with OXYCONTIN relative to oxycodone HCl. Thirty-three percent (n = 9) of subjects had a reduction of at least 30% in drug liking with OXYCONTIN compared to oxycodone HCl, and approximately 22% (n = 6) of subjects had a reduction of at least 50% in drug liking with OXYCONTIN compared to oxycodone HCl.

Figure 1: Percent Reduction Profiles for Emax of Drug Liking VAS for OXYCONTIN vs. Oxycodone HCl, N=27 Following Intranasal Administration

The results of a similar analysis of drug liking for finely crushed OXYCONTIN relative to finely crushed original OxyContin were comparable to the results of finely crushed OXYCONTIN relative to powdered oxycodone HCl. Approximately 43% (n = 12) of subjects had no reduction in liking with OXYCONTIN relative to original OxyContin. Approximately 57% (n = 16) of subjects had some reduction in drug liking, 36% (n = 10) of subjects had a reduction of at least 30% in drug liking, and approximately 29% (n = 8) of subjects had a reduction of at least 50% in drug liking with OXYCONTIN compared to original OxyContin.

Summary

The in vitro data demonstrate that OXYCONTIN has physicochemical properties expected to make abuse via injection difficult. The data from the clinical study, along with support from the in vitro data, also indicate that OXYCONTIN has physicochemical properties that are expected to reduce abuse via the intranasal route. However, abuse of OXYCONTIN by these routes, as well as by the oral route, is still possible.

Additional data, including epidemiological data, when available, may provide further information on the impact of the current formulation of OXYCONTIN on the abuse liability of the drug. Accordingly, this section may be updated in the future as appropriate.

OXYCONTIN contains oxycodone, an opioid agonist and Schedule II controlled substance with an abuse liability similar to other opioid agonists, legal or illicit, including fentanyl, hydromorphone, methadone, morphine, and oxymorphone. OXYCONTIN can be abused and is subject to misuse, addiction, and criminal diversion [see Warnings and Precautions (5.1), Drug Abuse and Dependence (9.1)].

9.3 Dependence

Both tolerance and physical dependence can develop during use of opioid therapy.

Tolerance is a physiological state characterized by a reduced response to a drug after repeated administration (i.e., a higher dose of a drug is required to produce the same effect that was once obtained at a lower dose).

Physical dependence is a state that develops as a result of a physiological adaptation in response to repeated drug use, manifested by withdrawal signs and symptoms after abrupt discontinuation or a significant dose reduction of a drug.

Withdrawal may be precipitated through the administration of drugs with opioid antagonist activity (e.g., naloxone, nalmefene), mixed agonist/antagonist analgesics (e.g., pentazocine, butorphanol, nalbuphine), or partial agonists (e.g., buprenorphine). Physical dependence may not occur to a clinically significant degree until after several days to weeks of continued use.

Do not rapidly reduce or abruptly discontinue OXYCONTIN in a patient physically dependent on opioids. Rapid tapering of OXYCONTIN in a patient physically dependent on opioids may lead to serious withdrawal symptoms, uncontrolled pain, and suicide. Rapid discontinuation has also been associated with attempts to find other sources of opioid analgesics, which may be confused with drug-seeking for abuse.

When discontinuing OXYCONTIN, gradually taper the dosage using a patient-specific plan that considers the following: the dose of OXYCONTIN the patient has been taking, the duration of treatment, and the physical and psychological attributes of the patient. To improve the likelihood of a successful taper and minimize withdrawal symptoms, it is important that the opioid tapering schedule is agreed upon by the patient. In patients taking opioids for an extended period of time at high doses, ensure that a multimodal approach to pain management, including mental health support (if needed), is in place prior to initiating an opioid analgesic taper [see Dosage and Administration (2.9), Warnings and Precautions (5.15)].

Infants born to mothers physically dependent on opioids will also be physically dependent and may exhibit respiratory difficulties and withdrawal signs [see Use in Specific Populations (8.1)].

10 OVERDOSAGE

Clinical Presentation

Acute overdose with oxycodone can be manifested by respiratory depression, somnolence progressing to stupor or coma, skeletal muscle flaccidity, cold and clammy skin, constricted pupils, and in some cases, pulmonary edema, bradycardia, hypotension, hypoglycemia, partial or complete airway obstruction, atypical snoring, and death. Marked mydriasis rather than miosis may be seen with hypoxia in overdose situations [see Clinical Pharmacology (12.2)]. Toxic leukoencephalopathy has been reported after opioid overdose and can present hours, days, or weeks after apparent recovery from the initial intoxication.

Treatment of Overdose

In case of overdose, priorities are the reestablishment of a patent and protected airway and institution of assisted or controlled ventilation, if needed. Employ other supportive measures (including oxygen, vasopressors) in the management of circulatory shock and pulmonary edema as indicated. Cardiac arrest or arrhythmias will require advanced life support measures.

For clinically significant respiratory or circulatory depression secondary to oxycodone overdose, administer an opioid overdose reversal agent such as naloxone or nalmefene.

Because the duration of reversal is expected to be less than the duration of action of oxycodone in OXYCONTIN, carefully monitor the patient until spontaneous respiration is reliably reestablished. OXYCONTIN will continue to release oxycodone and add to the oxycodone load for 24 to 48 hours or longer following ingestion, necessitating prolonged monitoring. If the response to an opioid overdose reversal agent is suboptimal or only brief in nature, administer additional reversal agent as directed by the product's prescribing information.

In an individual physically dependent on opioids, administration of the recommended usual dosage of the opioid overdose reversal agent will precipitate an acute withdrawal syndrome. The severity of the withdrawal symptoms experienced will depend on the degree of physical dependence and the dose of the reversal agent administered. If a decision is made to treat serious respiratory depression in the physically dependent patient, administration of the reversal agent should be initiated with care and by titration with smaller than usual doses of the reversal agent.

11 DESCRIPTION

OXYCONTIN® (oxycodone hydrochloride) extended-release tablets is an opioid agonist supplied in 10 mg, 15 mg, 20 mg, 30 mg, 40 mg, 60 mg, and 80 mg tablets for oral administration. The tablet strengths describe the amount of oxycodone per tablet as the hydrochloride salt. The structural formula for oxycodone hydrochloride is as follows:

C18 H21 NO4 ∙ HCl

MW 351.83

The chemical name is 4, 5α-epoxy-14-hydroxy-3-methoxy-17-methylmorphinan-6-one hydrochloride.

Oxycodone is a white, odorless crystalline powder derived from the opium alkaloid, thebaine. Oxycodone hydrochloride dissolves in water (1 g in 6 to 7 mL). It is slightly soluble in alcohol (octanol water partition coefficient 0.7).

The 10 mg, 15 mg, 20 mg, 30 mg, 40 mg, 60 mg and 80 mg tablets contain the following inactive ingredients: butylated hydroxytoluene (BHT), hypromellose, polyethylene glycol 400, polyethylene oxide, magnesium stearate, titanium dioxide.

The 10 mg tablets also contain hydroxypropyl cellulose.

The 15 mg tablets also contain black iron oxide, yellow iron oxide, and red iron oxide.

The 20 mg tablets also contain polysorbate 80 and red iron oxide.

The 30 mg tablets also contain polysorbate 80, red iron oxide, yellow iron oxide, and black iron oxide.

The 40 mg tablets also contain polysorbate 80 and yellow iron oxide.

The 60 mg tablets also contain polysorbate 80, red iron oxide and black iron oxide.

The 80 mg tablets also contain hydroxypropyl cellulose, yellow iron oxide and FD&C Blue #2/Indigo Carmine Aluminum Lake.

12 CLINICAL PHARMACOLOGY

12.1 Mechanism of Action

Oxycodone is a full opioid agonist and is relatively selective for the mu receptor, although it can bind to other opioid receptors at higher doses. The principal therapeutic action of oxycodone is analgesia. Like all full opioid agonists, there is no ceiling effect to analgesia for oxycodone. Clinically, dosage is titrated to provide adequate analgesia and may be limited by adverse reactions, including respiratory and CNS depression.

The precise mechanism of the analgesic action is unknown. However, specific CNS opioid receptors for endogenous compounds with opioid-like activity have been identified throughout the brain and spinal cord and are thought to play a role in the analgesic effects of this drug.

12.2 Pharmacodynamics

Effects on the Central Nervous System

Oxycodone produces respiratory depression by direct action on brain stem respiratory centers. The respiratory depression involves a reduction in the responsiveness of the brain stem respiratory centers to both increases in CO2 tension and electrical stimulation.

Oxycodone causes miosis, even in total darkness. Pinpoint pupils are a sign of opioid overdose but are not pathognomonic (e.g., pontine lesions of hemorrhagic or ischemic origin may produce similar findings). Marked mydriasis rather than miosis may be seen with hypoxia in overdose situations [see Overdosage (10)].

Effects on the Gastrointestinal Tract and Other Smooth Muscle

Oxycodone causes a reduction in motility associated with an increase in smooth muscle tone in the antrum of the stomach and duodenum. Digestion of food in the small intestine is delayed and propulsive contractions are decreased. Propulsive peristaltic waves in the colon are decreased, while tone may be increased to the point of spasm, resulting in constipation. Other opioid-induced effects may include a reduction in biliary and pancreatic secretions, spasm of sphincter of Oddi, transient elevations in serum amylase, and opioid-induced esophageal dysfunction (OIED).

Effects on the Cardiovascular System

Oxycodone produces peripheral vasodilation which may result in orthostatic hypotension or syncope. Manifestations of histamine release and/or peripheral vasodilation may include pruritus, flushing, red eyes, sweating, and/or orthostatic hypotension.

Effects on the Endocrine System

Opioids inhibit the secretion of adrenocorticotropic hormone (ACTH), cortisol, and luteinizing hormone (LH) in humans [see Adverse Reactions (6.2)]. They also stimulate prolactin, growth hormone (GH) secretion, and pancreatic secretion of insulin and glucagon.

Use of opioids for an extended period of time may influence the hypothalamic-pituitary-gonadal axis, leading to androgen deficiency that may manifest as low libido, impotence, erectile dysfunction, amenorrhea, or infertility. The causal role of opioids in the clinical syndrome of hypogonadism is unknown because the various medical, physical, lifestyle, and psychological stressors that may influence gonadal hormone levels have not been adequately controlled for in studies conducted to date [see Adverse Reactions (6.2)].

Effects on the Immune System

Opioids have been shown to have a variety of effects on components of the immune system in in vitro and animal models. The clinical significance of these findings is unknown. Overall, the effects of opioids appear to be modestly immunosuppressive.

Concentration –Efficacy Relationships

Studies in normal volunteers and patients reveal predictable relationships between oxycodone dosage and plasma oxycodone concentrations, as well as between concentration and certain expected opioid effects, such as pupillary constriction, sedation, overall subjective "drug effect", analgesia and feelings of relaxation.

The minimum effective analgesic concentration will vary widely among patients, especially among patients who have been previously treated with opioid agonists. The minimum effective analgesic concentration of oxycodone for any individual patient may increase over time due to an increase in pain, the development of a new pain syndrome, and/or the development of analgesic tolerance [see Dosage and Administration (2.1, 2.5)].

Concentration –Adverse Reaction Relationships

There is a relationship between increasing oxycodone plasma concentration and increasing frequency of dose-related opioid adverse reactions such as nausea, vomiting, CNS effects, and respiratory depression. In opioid-tolerant patients, the situation may be altered by the development of tolerance to opioid-related adverse reactions [see Dosage and Administration (2.1, 2.5)].

12.3 Pharmacokinetics

The activity of OXYCONTIN is primarily due to the parent drug oxycodone. OXYCONTIN is designed to provide delivery of oxycodone over 12 hours.

Cutting, breaking, chewing, crushing or dissolving OXYCONTIN impairs the controlled-release delivery mechanism and results in the rapid release and absorption of a potentially fatal dose of oxycodone.

Oxycodone release from OXYCONTIN is pH independent. The oral bioavailability of oxycodone is 60% to 87%. The relative oral bioavailability of oxycodone from OXYCONTIN to that from immediate-release oral dosage forms is 100%. Upon repeated dosing with OXYCONTIN in healthy subjects in pharmacokinetic studies, steady-state levels were achieved within 24-36 hours. Oxycodone is extensively metabolized and eliminated primarily in the urine as both conjugated and unconjugated metabolites. The apparent elimination half-life (t½) of oxycodone following the administration of OXYCONTIN was 4.5 hours compared to 3.2 hours for immediate-release oxycodone.

Absorption

About 60% to 87% of an oral dose of oxycodone reaches the central compartment in comparison to a parenteral dose. This high oral bioavailability is due to low pre-systemic and/or first-pass metabolism.

Plasma Oxycodone Concentration over Time

Dose proportionality has been established for OXYCONTIN 10 mg, 15 mg, 20 mg, 30 mg, 40 mg, 60 mg, and 80 mg tablet strengths for both peak plasma concentrations (Cmax) and extent of absorption (AUC) (see Table 6). Given the short elimination t½ of oxycodone, steady-state plasma concentrations of oxycodone are achieved within 24-36 hours of initiation of dosing with OXYCONTIN. In a study comparing 10 mg of OXYCONTIN every 12 hours to 5 mg of immediate-release oxycodone every 6 hours, the two treatments were found to be equivalent for AUC and Cmax, and similar for Cmin (trough) concentrations.

TABLE 6 Mean [% coefficient of variation]
Regimen | Dosage Form | AUC (ng∙hr/mL) [for single-dose AUC = AUC0-inf] | Cmax (ng/mL) | Tmax (hr)
Single Dose [data obtained while subjects received naltrexone, which can enhance absorption] | 10 mg | 136 [27] | 11.5 [27] | 5.11 [21]
 | 15 mg | 196 [28] | 16.8 [29] | 4.59 [19]
 | 20 mg | 248 [25] | 22.7 [25] | 4.63 [22]
 | 30 mg | 377 [24] | 34.6 [21] | 4.61 [19]
 | 40 mg | 497 [27] | 47.4 [30] | 4.40 [22]
 | 60 mg | 705 [22] | 64.6 [24] | 4.15 [26]
 | 80 mg | 908 [21] | 87.1 [29] | 4.27 [26]

Food Effects

Food has no significant effect on the extent of absorption of oxycodone from OXYCONTIN.

Distribution

Following intravenous administration, the steady-state volume of distribution (Vss) for oxycodone was 2.6 L/kg. Oxycodone binding to plasma protein at 37°C and a pH of 7.4 was about 45%. Once absorbed, oxycodone is distributed to skeletal muscle, liver, intestinal tract, lungs, spleen, and brain. Oxycodone has been found in breast milk [see Use in Specific Populations (8.2)].

Elimination

Metabolism

Oxycodone is extensively metabolized by multiple metabolic pathways to produce noroxycodone, oxymorphone and noroxymorphone, which are subsequently glucuronidated. Noroxycodone and noroxymorphone are the major circulating metabolites. CYP3A mediated N-demethylation to noroxycodone is the primary metabolic pathway of oxycodone with a lower contribution from CYP2D6 mediated O-demethylation to oxymorphone. Therefore, the formation of these and related metabolites can, in theory, be affected by other drugs [see Drug Interactions (7)].

Noroxycodone exhibits very weak anti-nociceptive potency compared to oxycodone, however, it undergoes further oxidation to produce noroxymorphone, which is active at opioid receptors. Although noroxymorphone is an active metabolite and present at relatively high concentrations in circulation, it does not appear to cross the blood-brain barrier to a significant extent. Oxymorphone is present in the plasma only at low concentrations and undergoes further metabolism to form its glucuronide and noroxymorphone. Oxymorphone has been shown to be active and possessing analgesic activity but its contribution to analgesia following oxycodone administration is thought to be clinically insignificant. Other metabolites (α- and ß-oxycodol, noroxycodol and oxymorphol) may be present at very low concentrations and demonstrate limited penetration into the brain as compared to oxycodone. The enzymes responsible for keto-reduction and glucuronidation pathways in oxycodone metabolism have not been established.

Excretion

Oxycodone and its metabolites are excreted primarily via the kidney. The amounts measured in the urine have been reported as follows: free and conjugated oxycodone 8.9%, free noroxycodone 23%, free oxymorphone less than 1%, conjugated oxymorphone 10%, free and conjugated noroxymorphone 14%, reduced free and conjugated metabolites up to 18%. The total plasma clearance was approximately 1.4 L/min in adults.

Specific Populations

Age: Geriatric Population

The plasma concentrations of oxycodone are only nominally affected by age, being 15% greater in elderly as compared to young subjects (age 21-45).

Age: Pediatric Population

In the pediatric age group of 11 years of age and older, systemic exposure of oxycodone is expected to be similar to adults at any given dose of OXYCONTIN.

Sex

Across individual pharmacokinetic studies, average plasma oxycodone concentrations for female subjects were up to 25% higher than for male subjects on a body weight-adjusted basis. The reason for this difference is unknown [see Use in Specific Populations (8.8)].

Hepatic Impairment

Data from a study involving 24 patients with mild to moderate hepatic dysfunction show peak plasma oxycodone and noroxycodone concentrations 50% and 20% higher, respectively, than healthy subjects. AUC values are 95% and 65% higher, respectively. Oxymorphone peak plasma concentrations and AUC values are lower by 30% and 40%. These differences are accompanied by increases in some, but not other, drug effects. The mean elimination t½ for oxycodone increased by 2.3 hours.

Renal Impairment

Data from a pharmacokinetic study involving 13 patients with mild to severe renal dysfunction (creatinine clearance <60 mL/min) showed peak plasma oxycodone and noroxycodone concentrations 50% and 20% higher, respectively, and AUC values for oxycodone, noroxycodone, and oxymorphone 60%, 50%, and 40% higher than normal subjects, respectively. This was accompanied by an increase in sedation but not by differences in respiratory rate, pupillary constriction, or several other measures of drug effect. There was an increase in mean elimination t½ for oxycodone of 1 hour.

Drug Interaction Studies

CYP3A4 Inhibitors

CYP3A4 is the major isoenzyme involved in noroxycodone formation. Co-administration of OXYCONTIN (10 mg single dose) and the CYP3A4 inhibitor ketoconazole (200 mg BID) increased oxycodone AUC and Cmax by 170% and 100%, respectively [see Drug Interactions (7)].

CYP3A4 Inducers

A published study showed that the co-administration of rifampin, a drug metabolizing enzyme inducer, decreased oxycodone AUC and Cmax values by 86% and 63%, respectively [see Drug Interactions (7)].

CYP2D6 Inhibitors

Oxycodone is metabolized in part to oxymorphone via CYP2D6. While this pathway may be blocked by a variety of drugs such as certain cardiovascular drugs (e.g., quinidine) and antidepressants (e.g., fluoxetine), such blockade has not been shown to be of clinical significance with OXYCONTIN [see Drug Interactions (7)].

13 NONCLINICAL TOXICOLOGY

13.1 Carcinogenesis, Mutagenesis, Impairment of Fertility

Carcinogenesis

Carcinogenic potential of oxycodone was evaluated in a 2-year oral gavage study in Sprague-Dawley rats. Oxycodone did not increase the incidence of tumors in male and female rats at doses up to 6 mg/kg/day (approximately 0.1 times and 0.5 times for males and females, respectively, a human oxycodone dose of 60 mg/day based on AUC comparison).

Mutagenesis

Oxycodone was genotoxic in the in vitro mouse lymphoma assay. Oxycodone was negative when tested at appropriate concentrations in the in vitro chromosomal aberration assay, the in vitro bacterial reverse mutation assay (Ames test), and the in vivo bone marrow micronucleus assay in mice.

Impairment of Fertility

In a study of reproductive performance, rats were administered a once daily gavage dose of the vehicle or oxycodone hydrochloride (0.5, 2, and 8 mg/kg/day). Male rats were dosed for 28 days before cohabitation with females, during the cohabitation and until necropsy (2-3 weeks post-cohabitation). Females were dosed for 14 days before cohabitation with males, during cohabitation and up to Gestation Day 6. Oxycodone hydrochloride did not affect reproductive function in male or female rats at any dose tested (up to 8 mg/kg/day), up to 1.3 times a human dose of 60 mg/day.

14 CLINICAL STUDIES

Adult Clinical Study

A double-blind, placebo-controlled, fixed-dose, parallel group, two-week study was conducted in 133 patients with persistent, moderate to severe pain, who were judged as having inadequate pain control with their current therapy. In this study, OXYCONTIN 20 mg, but not 10 mg, was statistically significant in pain reduction compared with placebo.

Pediatric Clinical Study

OXYCONTIN has been evaluated in an open-label clinical trial of 155 opioid-tolerant pediatric patients with moderate to severe chronic pain. The mean duration of therapy was 20.7 days (range 1 to 43 days). The starting total daily doses ranged from 20 mg to 100 mg based on the patient's prior opioid dose. The mean daily dose was 33.30 mg (range 20 to 140 mg/day). In an extension study, 23 of the 155 patients were treated beyond four weeks, including 13 for 28 weeks. Too few patients less than 11 years were enrolled in the clinical trial to provide meaningful safety data in this age group.

16 HOW SUPPLIED/STORAGE AND HANDLING

OXYCONTIN (oxycodone hydrochloride) extended-release tablets 10 mg are film-coated, round, white-colored, bi-convex tablets debossed with OP on one side and 10 on the other and are supplied as child-resistant closure, opaque plastic bottles of 100 (NDC 59011-410-10) and unit dose packaging with 10 individually numbered tablets per card; two cards per glue end carton (NDC 59011-410-20).

OXYCONTIN (oxycodone hydrochloride) extended-release tablets 15 mg are film-coated, round, gray-colored, bi-convex tablets debossed with OP on one side and 15 on the other and are supplied as child-resistant closure, opaque plastic bottles of 100 (NDC 59011-415-10) and unit dose packaging with 10 individually numbered tablets per card; two cards per glue end carton (NDC 59011-415-20).

OXYCONTIN (oxycodone hydrochloride) extended-release tablets 20 mg are film-coated, round, pink-colored, bi-convex tablets debossed with OP on one side and 20 on the other and are supplied as child-resistant closure, opaque plastic bottles of 100 (NDC 59011-420-10) and unit dose packaging with 10 individually numbered tablets per card; two cards per glue end carton (NDC 59011-420-20).

OXYCONTIN (oxycodone hydrochloride) extended-release tablets 30 mg are film-coated, round, brown-colored, bi-convex tablets debossed with OP on one side and 30 on the other and are supplied as child-resistant closure, opaque plastic bottles of 100 (NDC 59011-430-10) and unit dose packaging with 10 individually numbered tablets per card; two cards per glue end carton (NDC 59011-430-20).

OXYCONTIN (oxycodone hydrochloride) extended-release tablets 40 mg are film-coated, round, yellow-colored, bi-convex tablets debossed with OP on one side and 40 on the other and are supplied as child-resistant closure, opaque plastic bottles of 100 (NDC 59011-440-10) and unit dose packaging with 10 individually numbered tablets per card; two cards per glue end carton (NDC 59011-440-20).

OXYCONTIN (oxycodone hydrochloride) extended-release tablets 60 mg are film-coated, round, red-colored, bi-convex tablets debossed with OP on one side and 60 on the other and are supplied as child-resistant closure, opaque plastic bottles of 100 (NDC 59011-460-10) and unit dose packaging with 10 individually numbered tablets per card; two cards per glue end carton (NDC 59011-460-20).

OXYCONTIN (oxycodone hydrochloride) extended-release tablets 80 mg are film-coated, round, green-colored, bi-convex tablets debossed with OP on one side and 80 on the other and are supplied as child-resistant closure, opaque plastic bottles of 100 (NDC 59011-480-10) and unit dose packaging with 10 individually numbered tablets per card; two cards per glue end carton (NDC 59011-480-20).

STORAGE AND HANDLING

Store at 25°C (77°F); excursions permitted between 15°-30°C (59°-86°F) [see USP Controlled Room Temperature].

Store OXYCONTIN securely and dispose of properly [see Patient Counseling Information (17)].

Dispense in tight, light-resistant container.

17 PATIENT COUNSELING INFORMATION

Advise the patient to read the FDA-approved patient labeling (Medication Guide).

Storage and Disposal:

Because of the risks associated with accidental ingestion, misuse, and abuse, advise patients to store OXYCONTIN securely, out of sight and reach of children, and in a location not accessible by others, including visitors to the home. Inform patients that leaving OXYCONTIN unsecured can pose a deadly risk to others in the home [see Warnings and Precautions (5.1, 5.2), Drug Abuse and Dependence (9.2)].

Advise patients and caregivers that when medicines are no longer needed, they should be disposed of promptly. Expired, unwanted, or unused OXYCONTIN should be disposed of by flushing the unused medication down the toilet if a drug take-back option is not readily available. Inform patients that they can visit http://www.fda.gov/drugdisposal for a complete list of medicines recommended for disposal by flushing, as well as additional information on disposal of unused medicines.

Addiction, Abuse and Misuse

Inform patients that the use of OXYCONTIN, even when taken as recommended, can result in addiction, abuse, and misuse, which can lead to overdose and death [see Warnings and Precautions (5.1)]. Instruct patients not to share OXYCONTIN with others and to take steps to protect OXYCONTIN from theft or misuse.

Life-Threatening Respiratory Depression

Inform patients of the risk of life-threatening respiratory depression, including information that the risk is greatest when starting OXYCONTIN or when the dosage is increased, and that it can occur even at recommended dosages.

Educate patients and caregivers on how to recognize respiratory depression and emphasize the importance of calling 911 or getting emergency medical help right away in the event of a known or suspected overdose [see Warnings and Precautions (5.2), Overdosage (10)].

To guard against excessive exposure to OXYCONTIN by young children, advise caregivers to strictly adhere to recommended OXYCONTIN dosing.

Accidental Ingestion

Inform patients that accidental ingestion, especially by children, may result in respiratory depression or death [see Warnings and Precautions (5.2)].

Interactions with Benzodiazepines or Other CNS Depressants

Inform patients and caregivers that potentially fatal additive effects may occur if OXYCONTIN is used with benzodiazepines or other CNS depressants, including alcohol (e.g., non-benzodiazepine sedative/hypnotics, anxiolytics, tranquilizers, muscle relaxants, general anesthetics, antipsychotics, gabapentinoids [gabapentin or pregabalin], and other opioids), and not to use these concomitantly unless supervised by a healthcare provider [see Warnings and Precautions (5.3), Drug Interactions (7)].

Patient Access to an Opioid Overdose Reversal Agent for the Emergency Treatment of Opioid Overdose

Inform patients and caregivers about opioid overdose reversal agents (e.g., naloxone, nalmefene). Discuss the importance of having access to an opioid overdose reversal agent, especially if the patient has risk factors for overdose (e.g., concomitant use of CNS depressants, a history of opioid use disorder, or prior opioid overdose) or if there are household members (including children) or other close contacts at risk for accidental ingestion or opioid overdose.

Discuss with the patient the options for obtaining an opioid overdose reversal agent (e.g., prescription, over-the-counter, or as part of a community-based program) [see Dosage and Administration (2.2), Warnings and Precautions (5.3)].

Educate patients and caregivers on how to recognize the signs and symptoms of an overdose.

Explain to patients and caregivers that effects of opioid overdose reversal agents like naloxone and nalmefene are temporary, and that they must call 911 or get emergency medical help right away in all cases of known or suspected opioid overdose, even if an opioid overdose reversal agent is administered [see Overdosage (10)].

Advise patients and caregivers:

- how to treat with the overdose reversal agent in the event of an opioid overdose
- to tell family and friends about their opioid overdose reversal agent, and to keep it in a place where family and friends can access it in an emergency
- to read the Patient Information (or other educational material) that will come with their opioid overdose reversal agent. Emphasize the importance of doing this before an opioid emergency happens, so the patient and caregiver will know what to do

Hyperalgesia and Allodynia

Inform patients and caregivers not to increase opioid dosage without first consulting a clinician. Advise patients to seek medical attention if they experience symptoms of hyperalgesia, including worsening pain, increased sensitivity to pain, or new pain [see Warnings and Precautions (5.7), Adverse Reactions (6.2)].

Serotonin Syndrome

Inform patients that opioids could cause a rare but potentially life-threatening condition called serotonin syndrome resulting from concomitant administration of serotonergic drugs. Warn patients of the symptoms of serotonin syndrome and to seek medical attention right away if symptoms develop. Instruct patients to inform their healthcare provider if they are taking, or plan to take, serotonergic medications [see Drug Interactions (7)].

MAOI Interaction

Inform patients to avoid taking OXYCONTIN while using any drugs that inhibit monoamine oxidase. Patients should not start MAOIs while taking OXYCONTIN [see Drug Interactions (7)].

Important Administration Instructions

Instruct patients how to properly take OXYCONTIN, including the following:

- OXYCONTIN is designed to work properly only if swallowed intact. Taking cut, broken, chewed, crushed, or dissolved OXYCONTIN tablets can result in a fatal overdose [see Dosage and Administration (2.1)].
- OXYCONTIN tablets should be taken one tablet at a time [see Dosage and Administration (2.1)].
- Do not pre-soak, lick, or otherwise wet the tablet prior to placing in the mouth [see Dosage and Administration (2.1)].
- Take each tablet with enough water to ensure complete swallowing immediately after placing in the mouth [see Dosage and Administration (2.1)].

Important Discontinuation Instructions

In order to avoid developing withdrawal symptoms, instruct patients not to discontinue OXYCONTIN without first discussing a tapering plan with the prescriber [see Dosage and Administration (2.9)].

Driving or Operating Heavy Machinery

Inform patients that OXYCONTIN may impair the ability to perform potentially hazardous activities such as driving a car or operating heavy machinery. Advise patients not to perform such tasks until they know how they will react to the medication [see Warnings and Precautions (5.16)].

Constipation

Advise patients of the potential for severe constipation, including management instructions and when to seek medical attention [see Adverse Reactions (6), Clinical Pharmacology (12.2)].

Adrenal Insufficiency

Inform patients that OXYCONTIN could cause adrenal insufficiency, a potentially life-threatening condition. Adrenal insufficiency may present with non-specific symptoms and signs such as nausea, vomiting, anorexia, fatigue, weakness, dizziness, and low blood pressure. Advise patients to seek medical attention if they experience a constellation of these symptoms [see Warnings and Precautions (5.9)].

Hypotension

Inform patients that OXYCONTIN may cause orthostatic hypotension and syncope. Instruct patients how to recognize symptoms of low blood pressure and how to reduce the risk of serious consequences should hypotension occur (e.g., sit or lie down, carefully rise from a sitting or lying position) [see Warnings and Precautions (5.10, 5.11)].

Anaphylaxis

Inform patients that anaphylaxis has been reported with ingredients contained in OXYCONTIN. Advise patients how to recognize such a reaction and when to seek medical attention [see Contraindications (4), Adverse Reactions (6)].

Pregnancy

Neonatal Opioid Withdrawal Syndrome

Inform female patients of reproductive potential that use of OXYCONTIN for an extended period of time during pregnancy can result in neonatal opioid withdrawal syndrome, which may be life-threatening if not recognized and treated [see Warnings and Precautions (5.4), Use in Specific Populations (8.1)].

Embryo-Fetal Toxicity

Inform female patients of reproductive potential that OXYCONTIN can cause fetal harm and to inform their healthcare provider of a known or suspected pregnancy [see Use in Specific Populations (8.1)].

Lactation

Advise patients that breastfeeding is not recommended during treatment with OXYCONTIN [see Use in Specific Populations (8.2)].

Infertility

Inform patients that use of opioids for an extended period of time may cause reduced fertility. It is not known whether these effects on fertility are reversible [see Use in Specific Populations (8.3)].

Healthcare professionals can telephone Purdue Pharma's Medical Information Department (1-888-726-7535) for information on this product.

Purdue Pharma L.P.
Stamford, CT 06901-3431

©2025, Purdue Pharma L.P.

U.S. Patent Numbers 7,129,248; 8,808,741; 8,821,929; 8,894,987; 8,894,988; 9,073,933; 9,492,389; 9,492,391; 9,492,392; 9,492,393; 9,522,919; 9,763,886; 9,763,933; 9,770,416; 9,775,808; 9,775,810; 9,775,811; 9,777,011; 10,407,434; 10,696,684; 11,304,908 and 11,304,909.

Medication Guide
OXYCONTIN® (ox-e-KON-tin) (oxycodone hydrochloride) extended-release tablets, CII

OXYCONTIN is:
- A strong prescription pain medicine that contains an opioid (narcotic) that is used to manage severe and persistent pain, that requires an extended treatment period with a daily opioid pain medicine when other pain medicines do not treat your pain well enough or you cannot tolerate them.
- A long-acting (extended-release) opioid pain medicine that can put you at risk for overdose and death. Even if you take your dose correctly as prescribed, you are at risk for opioid addiction, abuse, and misuse that can lead to death.
- Not to be taken on an "as-needed" basis.
- Not for use in children less than 11 years of age and who are not already using opioid pain medicines regularly to manage pain severe enough to require daily around-the-clock long-term treatment of pain with an opioid.

Important information about OXYCONTIN:
- Get emergency help or call 911 right away if you take too much OXYCONTIN (overdose). When you first start taking OXYCONTIN, when your dose is changed, or if you take too much (overdose), serious or life-threatening breathing problems that can lead to death may occur. Ask your healthcare provider about medicines like naloxone or nalmefene that can be used in an emergency to reverse an opioid overdose.
- Taking OXYCONTIN with other opioid medicines, benzodiazepines, gabapentinoids (gabapentin or pregabalin), alcohol, or other central nervous system depressants (including street drugs) can cause severe drowsiness, decreased awareness, breathing problems, coma, and death.
- Never give anyone else your OXYCONTIN. They could die from taking it. Selling or giving away OXYCONTIN is against the law.
- Store OXYCONTIN securely, out of sight and reach of children, and in a location not accessible by others, including visitors to the home.

Do not take OXYCONTIN if you have:

- severe asthma, trouble breathing, or other lung problems.
- a bowel blockage or have narrowing of the stomach or intestines.

Before taking OXYCONTIN, tell your healthcare provider if you have a history of:

- head injury, seizures
- problems urinating

- liver, kidney, thyroid problems
- pancreas or gallbladder problems

- abuse of street or prescription drugs, alcohol addiction, opioid overdose, or mental health problems.

Tell your healthcare provider if you are:
- noticing your pain getting worse. If your pain gets worse after you take OXYCONTIN, do not take more OXYCONTIN without first talking to your healthcare provider. Talk to your healthcare provider if the pain that you have increases, if you feel more sensitive to pain, or if you have new pain after taking OXYCONTIN.
- pregnant or planning to become pregnant. Use of OXYCONTIN for an extended period of time during pregnancy can cause withdrawal symptoms in your newborn baby that could be life-threatening if not recognized and treated.
- breastfeeding. Not recommended during treatment with OXYCONTIN. It may harm your baby.
- living in a household where there are small children or someone who has abused street or prescription drugs. Taking prescription or over-the-counter medicines, vitamins, or herbal supplements. Taking OXYCONTIN with certain other medicines can cause serious side effects that could lead to death.

When taking OXYCONTIN:
- Do not change your dose. Take OXYCONTIN exactly as prescribed by your healthcare provider. Use the lowest dose possible for the shortest time needed.
- Take your prescribed dose every 12 hours at the same time every day. Do not take more than your prescribed dose in 12 hours. If you miss a dose, take your next dose at your usual time.
- Swallow OXYCONTIN whole. Do not cut, break, chew, crush, dissolve, snort, or inject OXYCONTIN because this may cause you to overdose and die.
- OXYCONTIN should be taken 1 tablet at a time. Do not pre-soak, lick, or wet the tablet before placing in your mouth to avoid choking on the tablet.
- Call your healthcare provider if the dose you are taking does not control your pain.
- Do not stop taking OXYCONTIN without talking to your healthcare provider.
- Dispose of expired, unwanted, or unused OXYCONTIN by promptly flushing down the toilet, if a drug take-back option is not readily available. Visit www.fda.gov/drugdisposal for additional information on disposal of unused medicines.

While taking OXYCONTIN DO NOT:
- Drive or operate heavy machinery until you know how OXYCONTIN affects you. OXYCONTIN can make you sleepy, dizzy, or lightheaded.
- Drink alcohol, or use prescription or over-the-counter medicines that contain alcohol. Using products containing alcohol during treatment with OXYCONTIN may cause you to overdose and die.

The possible side effects of OXYCONTIN are:
- constipation, nausea, sleepiness, vomiting, tiredness, headache, dizziness, abdominal pain. Call your healthcare provider if you have any of these symptoms and they are severe.

Get emergency medical help or call 911 right away if you have:
- trouble breathing, shortness of breath, fast heartbeat, chest pain, swelling of your face, tongue, or throat, extreme drowsiness, light-headedness when changing positions, feeling faint, agitation, high body temperature, trouble walking, stiff muscles, or mental changes such as confusion.

These are not all the possible side effects of OXYCONTIN. Call your healthcare provider for medical advice about side effects. You may report side effects to FDA at 1-800-FDA-1088. For more information, go to dailymed.nlm.nih.gov
Manufactured by: Purdue Pharma L.P., Stamford, CT 06901-3431, www.purduepharma.com or call 1-888-726-7535

This Medication Guide has been approved by the U.S. Food and Drug Administration.

Revised: 12/2025

OXYCONTIN® CII
(OXYCODONE HCl) EXTENDED-RELEASE TABLETS

OXYCONTIN® 10mg Tablets Label
NDC 59011-410-10

OXYCONTIN® 15mg Tablets Label
NDC 59011-415-10

OXYCONTIN® 20mg Tablets Label
NDC 59011-420-10

OXYCONTIN® 30mg Tablets Label
NDC 59011-430-10

OXYCONTIN® 40mg Tablets Label
NDC 59011-440-10

OXYCONTIN® 60mg Tablets Label
NDC 59011-460-10

OXYCONTIN® 80mg Tablets Label
NDC 59011-480-10